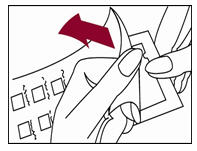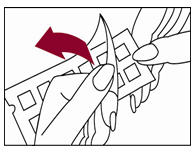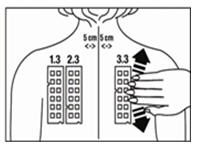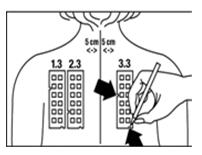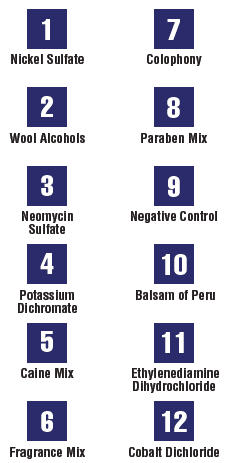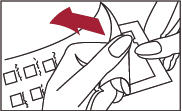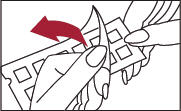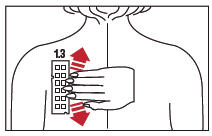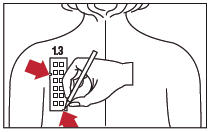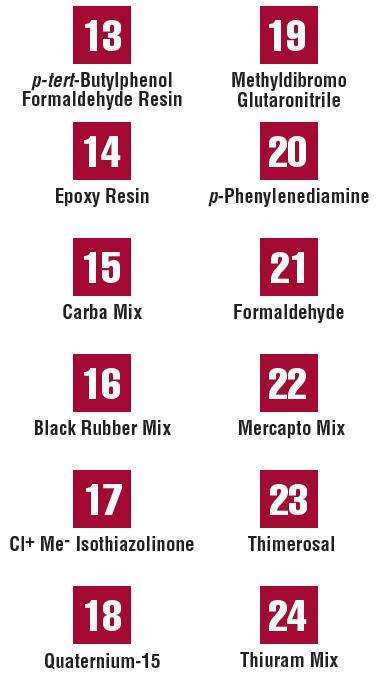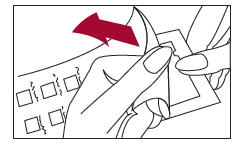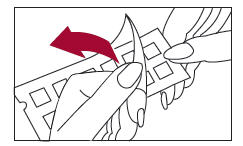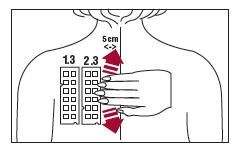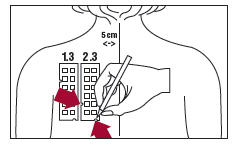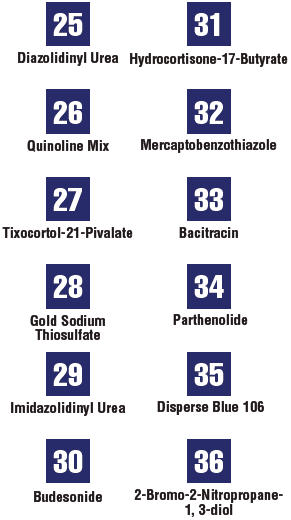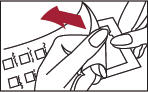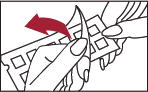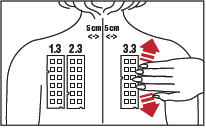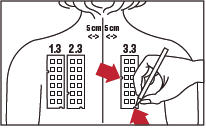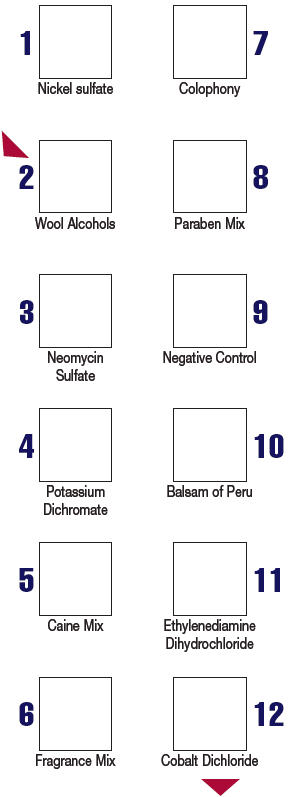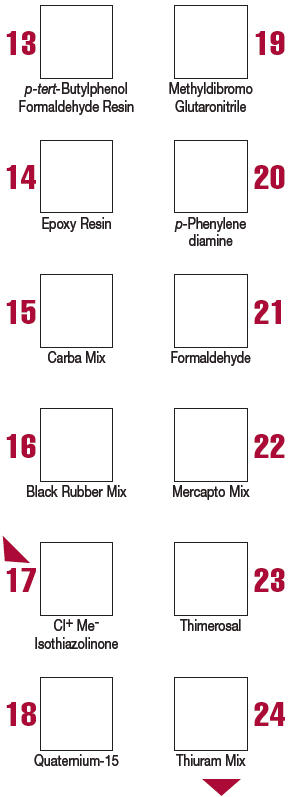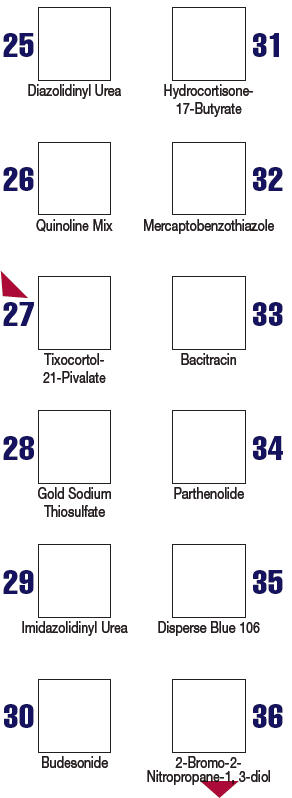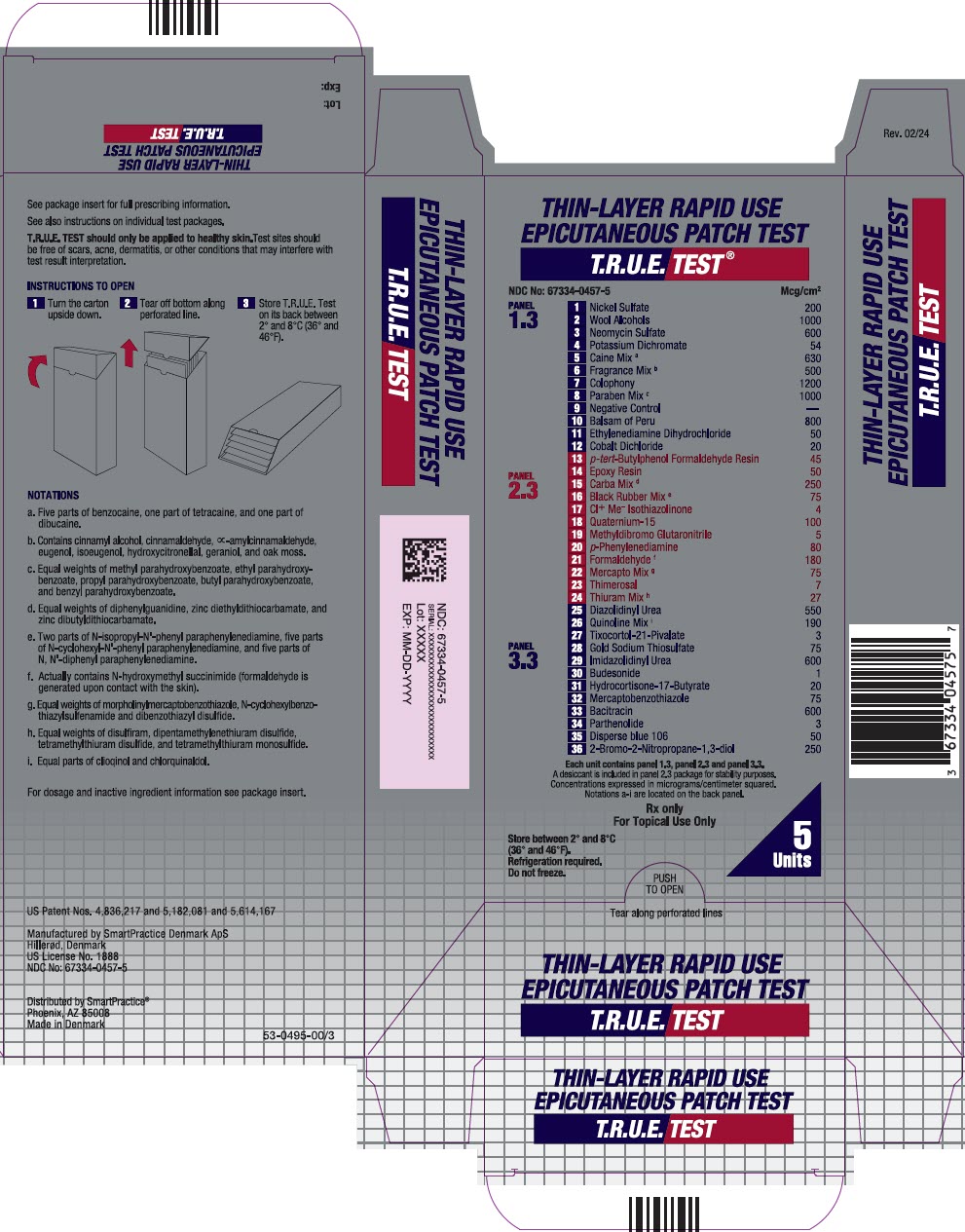 DRUG LABEL: T.R.U.E. Test

NDC: 67334-0457 | Form: KIT | Route: CUTANEOUS
Manufacturer: SmartPractice Denmark ApS
Category: other | Type: STANDARDIZED ALLERGENIC
Date: 20241115

ACTIVE INGREDIENTS: NICKEL SULFATE HEXAHYDRATE 36 ug/48 h; LANOLIN ALCOHOLS 810 ug/48 h; NEOMYCIN SULFATE 486 ug/48 h; POTASSIUM DICHROMATE 15.7 ug/48 h; BENZOCAINE 378 ug/48 h; TETRACAINE HYDROCHLORIDE 66 ug/48 h; DIBUCAINE HYDROCHLORIDE 66 ug/48 h; GERANIOL 81 ug/48 h; CINNAMALDEHYDE 41 ug/48 h; CINNAMYL ALCOHOL 63 ug/48 h; HYDROXYCITRONELLAL 63 ug/48 h; EUGENOL 41 ug/48 h; ISOEUGENOL 17 ug/48 h; .ALPHA.-AMYLCINNAMALDEHYDE 17 ug/48 h; EVERNIA PRUNASTRI 81 ug/48 h; ROSIN 972 ug/48 h; PROPYLPARABEN 162 ug/48 h; METHYLPARABEN 162 ug/48 h; ETHYLPARABEN 162 ug/48 h; BUTYLPARABEN 162 ug/48 h; BENZYLPARABEN 162 ug/48 h; BALSAM PERU 648 ug/48 h; ETHYLENEDIAMINE 18 ug/48 h; COBALTOUS CHLORIDE HEXAHYDRATE 4 ug/48 h; DIPENTAMETHYLENETHIURAM DISULFIDE 5.5 ug/48 h; P-TERT-BUTYLPHENOL-FORMALDEHYDE RESIN (LOW MOLECULAR WEIGHT) 36 ug/48 h; BISPHENOL A DIGLYCIDYL ETHER 32 ug/48 h; DIPHENYLGUANIDINE 68 ug/48 h; DITIOCARB ZINC 68 ug/48 h; ZINC DIBUTYLDITHIOCARBAMATE 68 ug/48 h; N-ISOPROPYL-N'-PHENYL-1,4-PHENYLENEDIAMINE 10 ug/48 h; N-CYCLOHEXYL-N'-PHENYL-P-PHENYLENEDIAMINE 25 ug/48 h; N,N'-DIPHENYL-P-PHENYLENEDIAMINE 25 ug/48 h; METHYLCHLOROISOTHIAZOLINONE 3 ug/48 h; QUATERNIUM-15 81 ug/48 h; METHYLDIBROMO GLUTARONITRILE 4 ug/48 h; P-PHENYLENEDIAMINE 65 ug/48 h; FORMALDEHYDE 146 ug/48 h; N-CYCLOHEXYL-2-BENZOTHIAZOSULFENAMIDE 20 ug/48 h; 2,2'-DITHIOBISBENZOTHIAZOLE 20 ug/48 h; MORPHOLINYLMERCAPTOBENZOTHIAZOLE 20 ug/48 h; THIMEROSAL 6 ug/48 h; TETRAMETHYLTHIURAM MONOSULFIDE 5.5 ug/48 h; THIRAM 5.5 ug/48 h; DISULFIRAM 5.5 ug/48 h; DIAZOLIDINYL UREA 446 ug/48 h; CLIOQUINOL 77 ug/48 h; CHLORQUINALDOL 77 ug/48 h; TIXOCORTOL PIVALATE 2 ug/48 h; GOLD SODIUM THIOSULFATE 23 ug/48 h; IMIDUREA 486 ug/48 h; BUDESONIDE 0.8 ug/48 h; HYDROCORTISONE BUTYRATE 16 ug/48 h; 2-MERCAPTOBENZOTHIAZOLE 61 ug/48 h; BACITRACIN 486 ug/48 h; PARTHENOLIDE 2 ug/48 h; DISPERSE BLUE 106 41 ug/48 h; BRONOPOL 203 ug/48 h
INACTIVE INGREDIENTS: HYDROXYPROPYL CELLULOSE (1600000 WAMW); POVIDONE, UNSPECIFIED; BETADEX; BUTYLATED HYDROXYANISOLE; BUTYLATED HYDROXYTOLUENE; HYDROXYPROPYL CELLULOSE (1600000 WAMW); POVIDONE, UNSPECIFIED; SODIUM BICARBONATE; SODIUM CARBONATE; POVIDONE, UNSPECIFIED; HYDROXYPROPYL CELLULOSE (1600000 WAMW)

HIGHLIGHTS OF PRESCRIBING INFORMATION

These highlights do not include all the information needed to use T.R.U.E. TEST safely and effectively. See full prescribing information for T.R.U.E. TEST.
T.R.U.E. TEST
Thin-Layer Rapid Use Epicutaneous Patch Test
For Topical Use Only
Initial U.S. Approval: 1994

RECENT MAJOR CHANGES

Indications and Usage (1) | 08/2017

1 INDICATIONS AND USAGE

T.R.U.E. TEST is an epicutaneous patch test indicated for use as an aid in the diagnosis of allergic contact dermatitis in persons 6 years of age and older whose history suggests sensitivity to one or more of the 35 allergens and allergen mixes included on the T.R.U.E. TEST panels. (1)

2 DOSAGE AND ADMINISTRATION

- For topical use only.

Apply the three adhesive panels of allergens and allergen mixes on healthy skin of the back. Remove panels and evaluate the skin 48 hours after application. Re-evaluate the skin 72 to 96 hours after application. (2)

3 DOSAGE FORMS AND STRENGTHS

Three adhesive panels consisting of 35 allergens and allergen mix patches and a negative control. Panel 1.3 contains 11 allergens and allergen mixes and a negative control. Panel 2.3 contains 12 allergens and allergen mixes. Panel 3.3 contains 12 allergens and allergen mixes. (3)

4 CONTRAINDICATIONS

- Do not apply to skin of patients with a history of severe allergic reaction (systemic and/or local) to any of the allergen components or inactive substances of T.R.U.E. TEST. (4)
- Do not apply to skin that is injured or inflamed. (4)

5 WARNINGS AND PRECAUTIONS

- Acute allergic reactions, including anaphylaxis, may occur. (5.1)
- Sensitization to one or more of the allergens may occur with initial or repeat testing. (5.2, 5.9)
- Extreme positive reactions, excited skin syndrome, tape reactions, irritant contact dermatitis, persistent reactions, and late reactions at the test site may occur. (5.3, 5.4, 5.5, 5.6, 5.7, 5.8)

6 ADVERSE REACTIONS

- In adults 18 years of age and older, the most common (occurring in >1% of the study population) adverse reactions were burning (25.4%), tape irritation (15.8%), persistent reactions (6.8%), erythema (5.7%), and hyper/hypopigmentation (4.9%).
- In children and adolescents 6 through 17 years of age, the most common (occurring in >1% of the study population) adverse reactions were itching (up to 61.2%), tape irritation (up to 50.0%), persistent reactions (4.6%), ectopic flare of pre-existing dermatitis (12.8%), burning (up to 10.5%), skin infections (1.8%), and skin reactions near a panel site (1.4%).

To report SUSPECTED ADVERSE REACTIONS, contact SmartPractice at 1-800-878-3837 or FDA at 1-800-FDA-1088 or www.fda.gov/medwatch.

7 DRUG INTERACTIONS

Patients on systemic or topical immunosuppressant therapy may have a diminished reaction to T.R.U.E. TEST. (7)

FULL PRESCRIBING INFORMATION

For topical use only.

1 INDICATIONS AND USAGE

T.R.U.E. TEST® is an epicutaneous patch test indicated for use as an aid in the diagnosis of allergic contact dermatitis (ACD) in persons 6 years of age and older whose history suggests sensitivity to one or more of the 35 allergens and allergen mixes included on the T.R.U.E. TEST panels.

2 DOSAGE AND ADMINISTRATION

2.1 Dose

T.R.U.E. TEST contains three adhesive panels consisting of 35 allergen and allergen mix patches and a negative control. See Description (11)for allergen types and amounts.

2.2 Administration

Application Instructions

T.R.U.E. TEST should only be applied to healthy skin. Test sites should be free of scars, acne, dermatitis, or other conditions that may interfere with test result interpretation. Avoid application of T.R.U.E. TEST panels to recently tanned or sun-exposed skin because this may increase the risk of false negatives. Avoid patch testing on patients for three (3) weeks after ultraviolet (UV) treatments, heavy sun, or tanning bed exposure. Avoid using alcohol or other irritating substances on the skin prior to testing. Avoid excessive sweating during the testing period to maintain sufficient adhesion to the skin. Avoid excessive physical activity to maintain sufficient adhesion and to prevent actual loss of patch test material. Avoid getting the panels and surrounding area wet. If excessive body hair exists at the test site, remove with an electric shaver (do not use razors). Very oily skin may be cleaned with mild soap and water prior to testing.

T.R.U.E. Test panels should be applied as follows:

Figure 1

Figure 2

Figure 3

Figure 4

1. Peel open the package and remove the test panel (Figure 1).

2. Remove the protective plastic covering from the test surface of the panel (Figure 2). Be careful not to touch the test allergens or allergen mixes.

3. Position test Panel 1.3 on the patient's back as shown in Figure 3. Allergen number 1 should be in the upper left corner. Avoid applying the panel on the margin of the scapula or directly over the midline of the spine. Ensure that each patch of the allergen panel is in contact with the skin by smoothing the panel outward from the center to the edge (as illustrated for Panel 3.3 in Figure 3).

4. With a medical marking pen, indicate on the skin the location of the two notches on the panel (as illustrated for Panel 3.3 in Figure 4).

5. Repeat the process with test Panel 2.3. Position the test Panel 2.3 beside Panel 1.3, on the left side of the patient's back so that the number 13 allergen is in the upper left corner. Apply test Panel 2.3 five (5) cm from the midline of the spine (Figure 3).

6. Repeat the process with Panel 3.3 positioning the panel on the right side of the patient's back so that the number 25 allergen is in the upper left corner. Apply test Panel 3.3 five (5) cm from the midline of the spine. (Figure 3)

7. If needed, hypoallergenic surgical tape, appropriate for patch testing, may be used for increased adhesion around the outside edges of the panels.

2.3 Timing of Test Readings

Schedule patients to return approximately 48 hours after patch test application to have the panels removed. Prior to removal of the panels, use a medical marking pen to remark the notches found on the panels. The patch test reaction on the patient's skin may be evaluated at 48 hours, but an additional reading(s) at 72 and/or 96 hours is necessary. Late positive reactions may occur 7 to 21 days after application of the panels. [see Warnings and Precautions (5.2)].

2.4 Interpretation Instructions

An identification template is provided for each of the three (3) panels for quick identification of any allergen that causes a reaction. To assure correct positioning, marks on the skin made with the medical marking pen should correlate with the notches on the template. The interpretation method, similar to the one recommended by the International Contact Dermatitis Research Group, is as follows:

 | ? | Doubtful reaction: faint macular erythema only
 | + | Weak positive reaction: non-vesicular with erythema, infiltration, possibly papules
 | ++ | Strong positive reaction: vesicular, erythema, infiltration, papules
 | +++ | Extreme positive reaction: bullous or ulcerative reaction
 | - | Negative reaction
 | IR | Irritant reaction: Pustules as well as patchy follicular or homogeneous erythema without infiltrations are usually signs of irritation and do not indicate allergy.

Itching is a subjective symptom that is expected to accompany a positive reaction.

False Negatives

False negative results may be due to insufficient patch contact with the skin and/or premature evaluation of the test. Repeat testing may be indicated. The effect of repetitive testing with T.R.U.E. TEST is unknown [see Warnings and Precautions (5.9)].

False Positives

A false positive result may occur when an irritant reaction cannot be differentiated from an allergic reaction. A positive test reaction should meet the criteria for an allergic reaction. If an irritant reaction cannot be distinguished from a true positive reaction or if a doubtful reaction is present, a retest may be considered. The effect of repetitive testing with T.R.U.E. TEST is unknown [see Warnings and Precautions (5.9)].

3 DOSAGE FORMS AND STRENGTHS

T.R.U.E. TEST contains three (3) adhesive panels consisting of 35 allergen and allergen mix patches and a negative control. Panel 1.3 contains 11 allergens and allergen mixes and a negative control. Panel 2.3 contains 12 allergens and allergen mixes. Panel 3.3 contains 12 allergens and allergen mixes. See Description (11)for allergen types and amounts.

4 CONTRAINDICATIONS

Do not apply to skin of patients with a history of severe allergic reaction (systemic and/or local) to any of the allergen components or inactive substances of T.R.U.E. TEST [see Description (11)].

Do not apply to skin that is injured or inflamed.

5 WARNINGS AND PRECAUTIONS

5.1 Acute Allergic Reactions

Acute allergic reactions, including anaphylaxis, may occur following the application of T.R.U.E. TEST. If a severe allergic reaction occurs, remove the T.R.U.E. TEST panel(s) and initiate appropriate medical treatment. Immediate contact urticaria may present within minutes to an hour after application in patients who are pre-sensitized to some allergens and may be local or generalized. Patients may be advised to remove the panels themselves if they experience systemic symptoms [see Patient Counseling Information (17)].

5.2 Sensitization

A negative patch test reaction, followed by a positive reaction 10 to 20 days after panel application, may indicate active sensitization. Active sensitization is confirmed upon retesting with a positive reaction occurring at the 72 and/or the 96 hour reading. If patients undergo a second series of patch tests immediately, select a new test site for T.R.U.E. TEST application. Alternatively, the same site may be retested after a 3-week clearing period, provided the site remains free of conditions that might affect test results [see Dosage and Administration (2.1)]. The safety and effectiveness of repetitive testing with T.R.U.E. TEST is unknown [see Warnings and Precautions (5.9)].

5.3 Extreme Positive Reactions

Extreme positive (+++) reactions that are bullous or ulcerative with pronounced erythema, infiltration, and coalescing vesicles may present in extremely sensitive patients [see Dosage and Administration (2.3)].

5.4 Excited Skin Syndrome (Angry Back)

Excited skin syndrome is a regional state of skin hyper-reactivity caused by the presence of a strong positive reaction which may result in other patch test sites to become reactive.

5.5 Tape Reactions

Reactions to the T.R.U.E. TEST tape or adhesive may occur. T.R.U.E. TEST panel tape and the individual patches are composed of polyester. The adhesive used in the panels is acrylate-based and processed to remove free monomers that may be allergenic [see Description (11)].

5.6 Irritant Contact Dermatitis

Patients may experience irritant contact dermatitis upon exposure to any of the allergens contained within T.R.U.E. TEST that cause direct damage to the skin at the test site. Recurrence of an irritant response is not limited to exposure to the specific allergens or allergen mixes, but may follow exposure to any chemical irritants.

5.7 Persistent Reactions

Positive reactions may persist from 7 days to months after panel application.

5.8 Late Reactions

Positive reactions may occur 7 to 21 days after application of the panels.

5.9 Repeat Testing

The safety and efficacy of repetitive testing with T.R.U.E. TEST is unknown. Sensitization or increased reactivity to one or more of the allergens may occur [see Warnings and Precautions (5.2)]. If patients undergo a second series of patch tests immediately, select a new test site for T.R.U.E. TEST application. Alternatively, the same site may be retested after a 3-week clearing period, provided the site remains free of conditions that might affect test results. [see Dosage and Administration (2.1)].

6 ADVERSE REACTIONS

In adults 18 years of age and older, the most common (occurring in >1% of the study population) adverse reactions were burning (25.4%), tape irritation (15.8%), persistent reactions (6.8%), erythema (5.7%), and hyper/hypopigmentation (4.9%). In children and adolescents 6 through 17 years of age, the most common (occurring in >1% of the study population) adverse reactions were itching (up to 61.2%), tape irritation (up to 50.0%), persistent reactions (4.6%), ectopic flare of pre-existing dermatitis (12.8%), burning (up to 10.5%), skin infections (1.8%), and skin reactions near a panel site (1.4%).

6.1 Clinical Trials Experience

Because clinical trials are conducted under widely varying conditions, adverse reaction rates observed in the clinical trials of a drug may not reflect the rates observed in clinical practice.

Adult Subjects 18 Years of Age and Older

Table 1 presents a summary of ten clinical trials conducted in adults in North America and Europe using T.R.U.E. TEST.

Table 1- Overview of Clinical Studies using T.R.U.E. TEST Among Adults 18 Years of Age and Older
Clinical Study Overview |  | Study 1 | Study 2 | Study 3 | Study 4 | Study 5 | Study 6 | Study 7 | Study 8 | Study 9 | Study 10 | Total
N |  | 127 | 121 | 119 | 50 | 130 | 128 | 200 | 235 | 49 | 9 | 1168
Age Range (years) |  | 19-79 | 18-77 | 19-76 | 19-82 | 19-86 | 20-83 | 19-78 | 18-85 | 18-68 | 36-76 | 18-86
Sex (% female) |  | 68% | 68% | 73% | 72% | 68% | 63% | 59% | 71% | 98% | 78% | 69%
Ethnicity | Caucasian | 86% | 88% | 83% | 92% | 85% | 88% | 97% | 91% | 98% | 100% | 83%
 | Black | 9% | 12% | 11% | 4% | 13% | 12% | 0% | 5% | 0% | 0% | 9%
 | Other | 5% | 1% | 6% | 4% | 2% | 0.8% | 3% | 4% | 2% | 0% | 7%
Allergens | Nickel sulfate | X |  | X | X |  |  |  |  | X
 | Wool alcohols |  | X | X | X
 | Neomycin sulfate | X |  | X | X |  |  |  |  | X
 | Potassium dichromate | X |  | X | X |  |  |  |  | X
 | Caine Mix | X |  | X | X |  |  |  |  | X
 | Fragrance Mix | X |  | X | X |  |  |  |  | X
 | Colophony | X |  | X | X |  |  |  |  | X
 | Paraben Mix |  | X | X | X
 | Balsam of Peru | X |  | X | X |  |  |  |  | X
 | Ethylenediamine dihydrochloride | X |  | X | X |  |  |  |  | X
 | Cobalt dichloride | X |  | X | X |  |  |  |  | X
 | p-tert-Butylphenol formaldehyde resin |  | X | X | X
 | Epoxy resin | X |  | X | X |  |  |  |  | X
 | Carba mix |  | X | X | X
 | Black rubber mix |  | X | X | X
 | Cl+ Me- Isothiazolinone |  | X | X | X
 | Quaternium-15 |  | X | X | X |  |  |  |  |  | X
 | Methyldibromo glutaronitrile |  |  |  |  |  |  |  | X
 | p-Phenylenediamine | X |  | X | X |  |  |  |  | X
 | Formaldehyde |  |  | X | X
 | Mercapto Mix |  | X | X | X
 | Thimerosal |  | X | X | X
 | Thiuram Mix | X |  | X | X |  |  |  |  | X
 | Diazolidinyl urea |  |  |  |  | X
 | Quinoline Mix |  | X | X | X
 | Tixocortol-21-pivalate |  |  |  |  |  | X | X
 | Gold Sodium Thiosulfate |  |  |  |  |  |  |  | X
 | Imidazolidinyl urea |  |  |  |  | X
 | Budesonide |  |  |  |  |  | X | X
 | Hydrocortisone-17-butyrate |  |  |  |  |  |  | X | X
 | Mercaptobenzothiazole |  | X | X | X
 | Bacitracin |  |  |  |  |  |  |  | X
 | Parthenolide |  |  |  |  |  |  |  | X
 | Disperse blue 106 |  |  |  |  |  |  |  | X
 | Bronopol |  |  |  |  |  |  |  | X

Table 2 summarizes the adverse reactions recorded in ten clinical studies. Subjects' adverse reactions were recorded on case report forms by study personnel. Adverse reactions were recorded during subject follow-up visits, which varied between 24 and/or 96 hours and/or Day 21 [see Clinical Studies (14)].

Table 2- Summary of Adverse Reactions Reported Among Adult Subjects 18 Years of Age and Older
 | Study 1 | Study 2 | Study 3 | Study 4 | Study 5 | Study 6 | Study 7 | Study 8 | Study 9 | Study 10 | Total (%)
N | 127 | 121 | 119 | 50 | 130 | 128 | 200 | 235 | 49 | 9 | 1168
Burning [Reported at 48 hours] | 12 | 6 | 9 | 16 | 50 | 51 | 25 | 123 | 5 | 0 | 297 (25.4)
Tape Irritation | 4 | 0 | 2 | 1 | 22 | 51 | 25 | 79 | 0 | 0 | 184 (15.8)
Persistent Reactions [Reported during follow up visit at Day 21] | 11 | 0 | 0 | 8 | 2 | 16 | 1 | 41 | 0 | 0 | 79 (6.8)
Erythema | 0 | 3 | 27 [Reported during follow up (4 to 80 days).] | 2 | 0 | 3 | 0 | 32 | 0 | 0 | 67 (5.7)
Hyper/Hypopigmentation | 11 | 2 | 8 | 6 | 1 | 7 | 0 | 14 | 8 | 0 | 57 (4.9)
Sensitization (possible) | 0 | 2 | 5 | 1 | 0 | 0 | 0 | ND | ND | ND | 8 (0.9) [n and % are based on the N of the studies where this data was collected.]
Late Reaction | 0 | 0 | 0 | 1 | 0 | 0 | 0 | 7 | 0 | 0 | 8 (0.7)
Scarring | 0 | 0 | 2 | ND | ND | ND | ND | ND | ND | ND | 2 (0.5)
Ectopic Flare | ND | ND | ND | ND | 1 | 0 | 1 | ND | ND | ND | 2(0.4)
ND=Not Done

Panel Adhesion:Problems with panel adhesion were observed during some of the clinical studies. Poor panel adhesion was defined as any panel that fell off prior to the 48-hour removal time, any test panel that was not in good contact with the skin, or if one or more of the patch test allergens were not in good contact with the skin as evidenced at the time of panel removal, 48 hours. If the panel fell off the back prior to the 48-hour removal time frame, the subject was excluded from the efficacy calculations (sensitivity and specificity) but not from the safety analysis. Over all studies, poor panel adhesion occurred 49 times (4.2%) (Table 3). In study 2, the poor adhesion was attributed to the particular lot of adhesive used to manufacture the clinical test tape.

Table 3- Incidence and Proportion of Poor Panel Adhesion Among Subjects 18 Years of Age and Older
 | Study 1 | Study 2 | Study 3 | Study 4 | Study 5 | Study 6 | Study 7 | Study 8 | Study 9 | Study 10 | Total
N | 127 | 121 | 119 | 50 | 130 | 128 | 200 | 235 | 49 | 9 | 1168
Poor Adhesion (%) | 0 (0.0) | 14 (11.6) | 2 (1.7) | 5 (10.0) | 1 (0.8) | 1 (0.8) | 0 (0.0) | 10 (4.3) | 12 (23.5) | 0 (0.0) | 49 (4.2)

Children and Adolescents 6 through 17 Years of Age

The safety of T.R.U.E. TEST in children and adolescents 6 through 17 years of age was evaluated in two open-label studies conducted in the US. In these studies, children and adolescents with suspected allergic contact dermatitis had three T.R.U.E. TEST panels applied to their backs and upper arms by investigators. Some of the panels were from previously approved versions of T.R.U.E. TEST. Subjects were instructed to keep the panels in place for 48 hours. Subjects were monitored for safety for 21 days after application of T.R.U.E. TEST panels. The safety monitoring plan included investigator's assessment of panel adhesion, tape irritation, and participant reporting of burning and itching (as a combined symptom) when panels were removed 2 days after application of T.R.U.E. TEST. Surveillance for late reactions, possible sensitization and persistent reactions occurred at Day 7 and 21. Unsolicited adverse events, serious adverse events and deaths were monitored for 21 days after patch application.

Pediatric Study 1 (NCT: 00795951)

In this prospective, single-center, open label study, 102 subjects were enrolled to evaluate the safety of T.R.U.E. TEST [see Clinical Studies (14.2)Table 7 for a list of the allergens and allergen mixes]. Of enrolled subjects, 52% were female, 39.2% were White, 31.4% were Hispanic, 6.9% were Black, 12.7% were Asian and 10.5% were of other racial/ethnic groups. The mean age of subjects was 11.6 years.

Pediatric Study 2 (NCT: 01797562)

In a prospective, multi-center, open-label study conducted in the US, up to 116 children and adolescents were enrolled to evaluate the safety of T.R.U.E. TEST [see Clinical Studies (14.2) Table 7for a list of the allergens and allergen mixes]. Of enrolled subjects, 69% were female, 37.9% were Hispanic or Latino, 28.5% were White, 11.2% were Asian, 6.0% were Black, and 16.4% were of other racial/ethnic groups. The mean age of subjects was 12.6 years. Table 4 summarizes adverse reactions occurring within 21 days after T.R.U.E. TEST application.

Table 4: Pediatric Study 2 [NCT: 01797562] : Adverse Reactions Occurring 2 Days after T.R.U.E. TEST Application in Children and Adolescents 6 through 17 Years of Age
Adverse Reactions | Any n (%) |  |  | Severe n (%)
 | Panel 1.3 N=54 [Fifty five subjects received Panel 1.3 and 61 subjects received Panel 1.2, which included 4 allergens with outdated formulations. Fifty four of the 55 subjects presented on day 2 as scheduled.] | Panel 2.3 N=114 [Of the 116 subjects who received T.R.U.E. TEST, 114 presented to visit 2 and had itching, burning, and tape irritation data documented.] | Panel 3.3 N=114 | Panel 1.3 N=54 | Panel 2.3 N=114 | Panel 3.3 N=114
Itching [Itching and burning were graded as none, mild/weak (minimal discomfort), moderate (definite discomfort), or severe (significantly bothersome, possible interference with sleep or daily activity).] | 31 (57.4) | 62 (54.4) | 72 (63.2) | 1 (1.9) | 7 (6.1) | 11 (9.7)
Burning | 3 (5.6) | 7 (6.1) | 12 (10.5) | 0 (0.0) | 0 (0.0) | 1 (0.9)
Tape irritation [Tape irritation was graded at Day 2 by investigators using a 4-point scale, including none, weak (faint to definite pink erythema), moderate (moderate erythema, definite redness), or severe (severe erythema, very intense redness).] | 27 (50.0) | 56 (49.1) | 53 (46.5) | 0 (0.0) | 1 (0.9) | 0 (0.0)

Across both pediatric studies (N=218), extreme positive reactions (+++, indicating a bullous or ulcerative reaction with pronounced erythema, infiltration, and coalescing vesicles) occurred in two subjects. Both extreme positive reactions occurred in response to metal allergens (nickel sulfate and gold sodium thiosulfate) by Day 3 and resolved by Day 21. Late positive reactions occurred in 2 subjects (0.9%) 21 days after T.R.U.E. TEST application to the following allergen: gold sodium thiosulfate (n=2). Persistent reactions occurred in 10 subjects (4.6%) 21 days after T.R.U.E. TEST application to the following allergens: bronopol (n=1), Cl+Me+isothiazolinone (n=1), diazolidinyl urea (n=1), gold sodium thiosulfate (n=6), nickel sulfate (n=2), and quaternium-15 (n=1). Ectopic flare of pre-existing dermatitis occurred in 28 (12.8%) of subjects. Of these cases, 1 (0.5%) was severe and 3 (1.4%) were complicated by skin infection. Skin reactions near a panel site were observed in 3 subjects (1.4%). No serious adverse events or deaths considered related to T.R.U.E. TEST occurred.

Panel Adhesion

In Pediatric Study 2, poor panel adhesion was observed in up to 11.3% of subjects who received T.R.U.E. TEST panels. Panel(s) fell off in up to 3.6% of participants in Pediatric Study 2.

6.2 Postmarketing Experience

The following additional adverse reactions have been identified during post-approval use of T.R.U.E. TEST. Because these reactions are continuously reported voluntarily from a population of uncertain size, it is not always possible to reliably estimate their frequency or establish a causal relationship to T.R.U.E. TEST exposure.

- Acute allergic reactions [see Warnings and Precautions (5.1)]
- Extreme positive reactions [see Warnings and Precautions (5.3)]
- Excited skin syndrome (Angry back) [see Warnings and Precautions (5.4)]
- Irritant contact dermatitis [see Warnings and Precautions (5.6)]

7 DRUG INTERACTIONS

7.1 Systemic Antihistamines

The effect of concomitant systemic antihistamine administration on the performance of patch testing with T.R.U.E. TEST is unknown.

7.2 Systemic Cyclosporins

The effect of concomitant or prior systemic cyclosporin administration on the performance of patch testing with T.R.U.E. TEST is unknown.

7.3 Systemic Glucocorticoids

Oral steroids may cause false negative results of patch testing with T.R.U.E. TEST. The risk of discontinuing or decreasing the dose of oral corticosteroids in order to perform the patch test must be weighed against the benefits of patch testing.

7.4 Topical Immunosuppressants and Immunomodulators

Avoid using test sites to which topical glucocorticoids, antihistamines, immunosuppressants, or immunomodulators are applied. The use of topical steroids or immunosuppressants at or near potential test sites should be avoided from at least one week prior to patch testing through the conclusion of patch testing.

8 USE IN SPECIFIC POPULATIONS

8.1 Pregnancy

Risk Summary

All pregnancies have a risk of birth defect, loss, or other adverse outcomes. In the US general population, the estimated background risk of major birth defects and miscarriage in clinically recognized pregnancies is 2-4% and 15-20%, respectively. There are no human or animal data to establish the presence or absence of T.R.U.E. TEST-associated risks during pregnancy.

8.2 Lactation

Risk Summary

It is not known whether the allergens in T.R.U.E. TEST are excreted in human milk. Data are not available to assess the effects of T.R.U.E. TEST on the breastfed child or on milk production/excretion. The developmental and health benefits of breastfeeding should be considered along with the mother's clinical need for T.R.U.E. TEST and any potential adverse effects on the breastfed child from T.R.U.E. TEST or from the underlying maternal condition.

8.4 Pediatric Use

Safety and effectiveness of T.R.U.E. TEST have not been established in persons younger than 6 years of age.

8.5 Geriatric Use

Clinical studies of T.R.U.E. TEST did not include sufficient numbers of subjects aged 65 years and over to determine whether they respond differently from younger subjects.

11 DESCRIPTION

Thin-layer Rapid Use Epicutaneous Patch Test, T.R.U.E. TEST ,is a ready-to-use allergen patch test system consisting of 35 allergen and allergen mix patches, containing 58 allergenic substances, and a negative control.

Each test consists of the following:

Panel-The panel consists of three pieces of surgical tape (5.2 × 13.0 cm), each with 12 polyester patches of approximately 0.81 cm^2. Each patch is coated with a film containing a uniformly dispersed specific allergen or allergen mix. The negative control, located on Panel 1.3, is an uncoated polyester patch.

Tape-The panel tape is composed of polyester. The adhesive used in the panels is acrylate-based. There is no natural rubber latex, rubber components, balsams or rosins in the adhesive or tape. Acrylate adhesives are processed to remove free monomers that may be allergenic.

Foil Pouch-Each test panel is covered by a protective sheet and sealed in a pouch of laminated foil.

Desiccant-A desiccant is included in the foil pouch of Panel 2.3 for stability purposes.

Inactive Ingredients-The allergens are homogenized in one or more of the following materials to produce the allergen films that coat the patches: hydroxypropyl cellulose (HPC), povidone (PVP), povidone with butylhydroxyanisole (BHA) and butylhydroxytoluene (BHT), povidone with sodium bicarbonate and sodium carbonate (PSBSC), and hydroxypropylcellulose with β-cyclodextrin (HPCβ).

The individual components of T.R.U.E. TEST Panels 1.3, 2.3, and 3.3 are listed below along with a quantitative description of each patch formulation. Panel 1.3 contains 11 allergens or allergen mixes and a negative control, Panel 2.3 contains 12 allergens or allergen mixes, and Panel 3.3 contains 12 allergens or allergen mixes.

11.1 Allergens on Panel 1.3

Nickel Sulfate (Position 1):

Nickel sulfate hexahydrate (purity ≥98.5%) is used to formulate this patch. The active allergenic component is nickel. The gel vehicle is hydroxypropyl cellulose. The product is formulated to contain 200 mcg/cm^2of nickel sulfate hexahydrate, which corresponds to 36 mcg of nickel per patch. Nickel is one of the most common metals in the environment and is found in most metal and metal-plated objects.

Wool Alcohols (Lanolin) (Position 2):

Wool alcohols, USP are a natural product obtained from the fleece of sheep. This allergen is a highly complex mixture of alcohols containing cholesterol, lanosterol, agnosterol, and their dihydro derivatives as well as straight and branched chain aliphatic alcohols. The active allergenic component has not been identified. The gel vehicle is povidone. The product is formulated to contain 1000 mcg/cm^2of wool alcohols, which corresponds to 810 mcg of wool alcohols per patch. Wool alcohols are a common constituent of many ointments, creams, lotions, and soaps.

Neomycin Sulfate (Position 3):

Neomycin sulfate, USP an antibiotic drug substance, is used to formulate this patch. The gel vehicle is povidone. The product is formulated to contain 600 mcg/cm^2of neomycin sulfate, which corresponds to 486 mcg of neomycin sulfate per patch. Neomycin is a common antibiotic found in topical antibiotic creams, lotions, ointments, eye drops, and ear drops.

Potassium Dichromate (Position 4):

Potassium dichromate (purity ≥98.5%) is used to formulate this patch. The active allergenic component is chromium. The gel vehicle is povidone. The product is formulated to contain 54 mcg/cm^2of potassium dichromate, which corresponds to 15.7 mcg of chromium per patch. Chromium is found in cement, as well as in many industrial chemicals.

Caine Mix (Position 5):

Caine mix is composed of three drug substances: benzocaine, USP (purity ≥98.0); tetracaine hydrochloride, USP (purity ≥98.5); and dibucaine hydrochloride, USP (purity ≥97.0). The gel vehicle is povidone. The product is formulated to contain 630 mcg/cm^2of caine mix, which corresponds to 510 mcg of caine mix per patch (378 mcg of benzocaine, 66 mcg of tetracaine, and 66 mcg of dibucaine). Benzocaine, tetracaine, and dibucaine are found in many topical anesthetic medications.

Fragrance Mix (Position 6):

Fragrance mix is composed of eight substances: geraniol (purity ≥95%, identity of impurities unknown); cinnamaldehyde (purity ≥95%, contains trace amounts of cinnamyl alcohol); hydroxycitronellal (purity ≥95%, identity of impurities unknown); cinnamyl alcohol (purity ≥95%, identity of impurities unknown); eugenol, USP (purity ≥95%, identity of impurities unknown); isoeugenol (purity ≥88%, identity of impurities unknown); α-amylcinnamaldehyde (purity ≥90%, identity of impurities unknown); and oak moss. Oak moss, a dark green sticky paste, is a solvent extract of the lichen Evernia prunastri. The chemical composition is very complex. The acid fraction (95% of the extracted material) is made up of depsides including atranorin, evernic acid, usnic acid, chloratranorin, and degradation products of these depsides. Atranorin is suspected as a prime allergenic component, and its peak (measured with gas chromatography) is used to determine the amount of oak moss in the fragrance mix patch. The gel vehicles used in this patch are povidone and β-cyclodextrin. The product is formulated to contain 500 mcg/cm^2of fragrance mix, which corresponds to 405 mcg of fragrance mix per patch (approximately 81 mcg of geraniol, approximately 41 mcg of cinnamaldehyde, approximately 63 mcg of hydroxycitronellal, approximately 63 mcg of cinnamyl alcohol, approximately 41 mcg of eugenol, approximately 17 mcg of isoeugenol, approximately 17 mcg of α-amylcinnamaldehyde, and approximately 81 mcg of oak moss). The components of fragrance mix are commonly used in toiletries, fragrances, and flavorings.

Colophony (Position 7):

Colophony is produced from the resin of the pine trees Pinus massoniana and Pinus tabuliformis. It is translucent, pale yellow or brownish yellow, brittle, and glassy in appearance. Colophony consists of 75% to 85% resin acids, 10% neutral fractions (i.e., terpenes), with the remaining part oxidation products. Oxidation products of abietic acid and other resin acids have been identified as the active allergenic components. The ultraviolet absorbance measurement of one of the primary components, abietic acid, is used to quantify colophony. The gel vehicle is povidone. BHA and BHT are added in equal amounts of 11 mcg per patch as antioxidants. The product is formulated to contain 1200 mcg/cm^2of colophony, which corresponds to 972 mcg of colophony per patch. Colophony is found in adhesives, sealants, and pine oil cleaners.

Paraben Mix (Position 8):

Paraben mix contains the five ester derivatives of parahydroxybenzoic acid: methyl, USP; ethyl, USP; propyl, USP; butyl, USP; and benzyl parahydroxybenzoate in equal parts (purity of each derivative ≥ 98.0%). The gel vehicle is povidone. The product is formulated to contain 1000 mcg/cm^2of paraben mix, which corresponds to 810 mcg of paraben mix per patch. The components of paraben mix can be found in cosmetics, dermatological creams, and paste bandages.

Negative Control (Position 9):

The negative control is an uncoated polyester patch.

Balsam of Peru (Position 10):

Balsam of peru is a resin from a South American tree, Myroxylon balsamum pereirae. The resin consists of a mixture of fragrances and other substances that have not all been identified. Balsam of peru patch content is measured by gas chromatography of its two major constituents, benzyl cinnamate and benzyl benzoate. Several components of Balsam of peru have been identified as allergens, including cinnamic acid, benzyl alcohol, and vanillin. The gel vehicle is povidone. This patch is formulated to contain 800 mcg/cm^2of Balsam of peru resin, which corresponds to 648 mcg of Balsam of peru resin per patch. This resin is found in many cosmetics and perfumes and is also used as a flavoring agent in cough syrups, lozenges, chewing gum, and candies.

Ethylenediamine Dihydrochloride (Position 11):

Ethylenediamine dihydrochloride (purity ≥98.5%) is used to formulate this patch. The active allergenic component is ethylenediamine. The gel vehicle is povidone. The product is formulated to contain 50 mcg/cm^2of ethylenediamine dihydrochloride, which corresponds to 18 mcg of ethylenediamine per patch. Ethylenediamine is used as a stabilizer, emulsifier, and preservative in topical fungicides, antibiotic creams, eye drops, and nose drops.

Cobalt Dichloride (Position 12):

Cobalt dichloride hexahydrate (purity ≥98.5%) is used to formulate this patch. The active allergenic component is cobalt. The gel vehicle is hydroxypropyl cellulose. The product is formulated to contain 20 mcg/cm^2of cobalt dichloride hexahydrate, which corresponds to 4 mcg of cobalt per patch. Cobalt is found in metal-plated objects and costume jewelry.

11.2 Allergens on Panel 2.3

p-tert-Butylphenol Formaldehyde Resin (Position 13):

p-tert-Butylphenol formaldehyde resin (purity ≥95%) is used to formulate this patch. The active allergenic components have been identified as p-tert-butylphenol formaldehyde and numerous other compounds. The gel vehicle is hydroxypropyl cellulose. The product is formulated to contain 45 mcg/cm^2of p-tert-butylphenol formaldehyde resin, which corresponds to 36 mcg of p-tert-butylphenol formaldehyde resin per patch. This resin is found in many waterproof glues used in the leather goods, furniture, and shoe industries.

Epoxy Resin (Position 14):

Epoxy resin, a clear viscous liquid, is used to formulate this patch. It consists of 75% to 85% diglycidylether of bisphenol A, the active allergenic component, which is a monomer used for the preparation of polymer epoxy resins. The remaining part consists of the dimer and the trimer. The gel vehicle is hydroxypropyl cellulose. This patch is formulated to contain 50 mcg/cm^2of epoxy resin, which corresponds to 32 mcg of diglycidylether of bisphenol A per patch. This resin is found in adhesives, surface coatings, and paints.

Carba Mix (Position 15):

Carba mix contains three chemicals used to stabilize rubber products: diphenylguanidine (purity ≥96%), zincdibutyldithiocarbamate (purity ≥96%), and zincdiethyldithiocarbamate (purity ≥96%) in equal parts. The gel vehicle is hydroxypropyl cellulose. The product is formulated to contain 250 mcg/cm^2of carba mix, which corresponds to 203 mcg of carba mix per patch. These chemical stabilizers and accelerators are found in many rubber products, pesticides, and some glues.

Black Rubber Mix (Position 16):

Black rubber mix contains the antioxidant and antiozonate chemicals N-isopropyl-N'-phenyl paraphenylenediamine (purity ≥95%), N-cyclohexyl-N'-phenyl paraphenylenediamine (purity ≥90%), and N, N'-diphenyl paraphenylenediamine (purity ≥90%) in the ratio 2:5:5. The gel vehicle is povidone. The product is formulated to contain 75 mcg/cm^2of black rubber mix, which corresponds to 61 mcg of black rubber mix per patch. The components of black rubber mix are found in almost all black rubber products, such as tires, handles, and hoses.

Cl+ Me- Isothiazolinone (MCI/MI) (Position 17):

Cl+ Me- Isothiazolinone is an antibacterial preservative that consists of two active ingredients, 5-chloro-2-methyl-4-isothiazolin-3-one (1.05% to 1.25% w/w) and 2-methyl-4-isothiazolin-3-one (0.25% to 0.40% w/w) in a 3:1 ratio at a concentration of 1.5% in aqueous magnesium salts. The gel vehicle is povidone. The product is formulated to contain 4 mcg/cm^2of Cl+ Me- iso-thiazolinone, which corresponds to 3 mcg of Cl+ Me- isothiazolinone per patch. This preservative is found in many shampoos, creams, lotions, and other skin care products.

Quaternium-15 (Q-15) (Position 18):

Quaternium-15, 1-(3-chloroallyl)-3,5,7,-triaza-1-azonium-adamantane chloride (purity ≥94%), is a preservative. The gel vehicle is hydroxypropyl cellulose. The product is formulated to contain 100 mcg/cm^2of Quaternium-15, which corresponds to 81 mcg of Quaternium-15 per patch. This preservative is found in creams, lotions, shampoos, soaps, and other cosmetics and skin care products.

Methyldibromo Glutaronitrile (MDBGN) (Position 19):

Methyldibromo Glutaronitrile, 1,2-Dibromo-2,4-dicyanobutane (purity ≥95%), is a component of the preservative Euxyl K400. The gel vehicle is povidone. The patch is formulated to contain 5 mcg/cm^2of methyldibromo glutaronitrile, which corresponds to 4 mcg of methyldibromo glutaronitrile per patch. Methyldibromo glutaronitrile is commonly used in cosmetic and personal care products such as body creams, facial and hand lotions, sun screens, baby lotions, shower gels, ultrasonic gel, toilet paper, shampoos, and massage oils. It is also found in cutting oils, drilling oils, glues, and coolants.

p-Phenylenediamine (Position 20):

p-Phenylenediamine (purity ≥97.5%), a blue-black aniline dye, is used to formulate this patch. The gel vehicle is povidone. The product is formulated to contain 80 mcg/cm^2of p-phenylenediamine, which corresponds to 65 mcg of p-phenylenediamine per patch. This dye is found most often in permanent and semipermanent hair dyes.

Formaldehyde (Position 21):

Formaldehyde is released from the proallergen N-hydroxymethyl succinimide, which is cleaved into succinimide and formaldehyde when it comes in contact with the transepidermal water on the surface of the skin. Formaldehyde is the active allergenic compound. The content of formaldehyde in the proallergen is 22.1% to 24.1%. The gel vehicle is povidone with sodium bicarbonate and sodium carbonate. The product is formulated to contain 180 mcg/cm^2of formaldehyde, which corresponds to 146 mcg of formaldehyde per patch. Formaldehyde is found in many building materials and plastic industries.

Mercapto Mix (Position 22):

Mercapto mix is composed of three chemical accelerators that are benzothiazole sulfenamide derivatives. N-cyclohexylbenzothiazyl-sulfenamide (purity ≥85%), dibenzothiazyl disulfide (purity ≥97%), and morpholinylmercaptobenzothiazole (purity ≥85%) are present in equal parts. The gel vehicle is povidone. The product is formulated to contain 75 mcg/cm^2of mercapto mix, which corresponds to 61 mcg of mercapto mix per patch. This group of chemicals is found in many rubber products, such as shoes, gloves, and elastics.

Thimerosal (Position 23):

Thimerosal, USP (purity ≥97%) is a preservative that contains mercury. The gel vehicle is povidone. The product is formulated to contain 7 mcg/cm^2of thimerosal, which corresponds to 6 mcg of thimerosal per patch. Thimerosal is found in some cosmetics, nose drops, eardrops, and vaccines.

Thiuram Mix (Position 24):

Thiuram mix is composed of four substances in equal parts: tetramethylthiuram monosulfide (purity ≥95%, contains small amounts of tetramethylthiuram disulfide); tetramethylthiuram disulfide (purity ≥95%, contains small amounts of tetramethylthiuram monosulfide); disulfiram, USP (tetraethylthiuram disulfide, purity ≥98.0%); and dipentamethylenethiuram disulfide (purity ≥95%, impurities unknown). The components of thiuram mix can chemically interact, resulting in the formation of mixed disulfides. Thiuram monosulfides and disulfides are the active allergens. The gel vehicle is povidone. The product is formulated to contain 27 mcg/cm^2of thiuram mix, which corresponds to 22 mcg of thiuram mix per patch (5.5 mcg of tetramethylthiuram monosulfide, 5.5 mcg of tetramethylthiuram disulfide, 5.5 mcg of disulfiram, and 5.5 mcg of dipentamethylenethiuram disulfide). These antimicrobial, accelerator, and antioxidant substances are found in many rubber products.

11.3 Allergens on Panel 3.3

Diazolidinyl Urea (DU) (Germall®II) (Position 25):

Diazolidinyl urea is a complex mixture. The gel vehicle is povidone. The product is formulated to contain 550 mcg/cm^2of diazolidinyl urea, which corresponds to 446 mcg of diazolidinyl urea per patch. Diazolidinyl urea is a preservative found in cosmetics.

Quinoline Mix (Position 26):

Quinoline mix is composed of two chemical germicides. Clioquinol, USP (purity ≥93.0%) and clorquinaldol (purity ≥95%), which are present in equal parts. The product is formulated to contain 190 mcg/cm^2of quinoline mix, which corresponds to 154 mcg of quinoline mix per patch. The gel vehicle is povidone. Quinolines are found in paste bandages, medicated creams, and ointments.

Tixocortol-21-Pivalate (TIX) (Position 27):

Tixocortol-21-pivalate (purity ≥95%) is a corticosteroid. The gel vehicle is povidone. The product is formulated to contain 3 mcg/cm^2of tixocortol-21-pivalate, which corresponds to 2 mcg of tixocortol-21-pivalate per patch. Tixocortol-21-pivalate is found in some medical products. Patch testing with tixocortol-21-pivalate may be used to assist in the diagnosis of allergic contact dermatitis due to corticosteroids in Group A, based on the classification of topical corticosteroids by cross-reactivity.

Gold Sodium Thiosulfate (GST) (Position 28):

Gold sodium thiosulfate (purity ≥ 90%) is a fairly common sensitizer with elicitation of symptoms linked to gold in jewelry, occupational exposure to gold, previous rheumatoid arthritis treatment, dental restorations, and gold-plated intracoronary stents. The gel vehicle is hydroxypropyl cellulose and the product is formulated to contain 75 mcg/cm^2of gold sodium thiosulfate, which corresponds to 23 mcg of gold per patch.

Imidazolidinyl Urea (IMID) (Germall®115) (Position 29):

Imidazolidinyl urea is a complex mixture. The gel vehicle is povidone. The product is formulated to contain 600 mcg/cm^2of imidazolidinyl urea, which corresponds to 486 mcg of imidazolidinyl urea per patch. Imidazolidinyl urea is a preservative found in cosmetics.

Budesonide (BUD) (Position 30):

Budesonide, USP (purity ≥98.0%) is a corticosteroid. The gel vehicle is povidone. The product is formulated to contain 1 mcg/cm^2of budesonide, which corresponds to 0.8 mcg of budesonide per patch. Budesonide is found in topical medicinal and anti-inflammatory products. Patch testing with budesonide may be used to assist in the diagnosis of allergic contact dermatitis due to corticosteroids in Group B and to certain esters in Group D, based on the classification of topical corticosteroids by cross-reactivity.

Hydrocortisone-17-Butyrate (H-17-B) (Position 31):

Hydrocortisone-17-butyrate, USP (purity ≥ 97.0%) is a mid-potent (Group D2) corticosteroid, most commonly used to treat inflammatory skin disease and psoriasis. The gel vehicle is povidone. The product is formulated to contain 20 mcg/cm^2of hydrocortisone-17-butyrate, which corresponds to 16 mcg of hydrocortisone-17-butyrate per patch. Hydrocortisone-17-butyrate is found in many topical over-the-counter (OTC) and prescription pharmaceuticals.

Mercaptobenzothiazole (Position 32):

Mercaptobenzothiazole (purity ≥98.5%) is a vulcanization accelerator used in rubber products. The gel vehicle is povidone. The product is formulated to contain 75 mcg/cm^2of mercaptobenzothiazole, which corresponds to 61 mcg of mercaptobenzothiazole per patch. This chemical is found in many rubber products, some adhesives, and is used as an industrial anticorrosive agent.

Bacitracin (Position 33):

Bacitracin, USP is an antibiotic used for postoperative and general wound care and is considered a frequent sensitizer. The gel vehicle is hydroxypropyl cellulose and the product is formulated to contain 600 mcg/cm^2of bacitracin which corresponds to 486 mcg of bacitracin per patch. Bacitracin is often a first-line topical remedy for cutaneous injuries and dermatoses as well as for many eye and ear disorders.

Parthenolide (Position 34):

Parthenolide (purity ≥ 95%) is a sesquiterpene lactone, which occurs naturally in thousands of plants including Daisies, Feverfew, and Magnolia. The gel vehicle is povidone and the product is formulated to contain 3 mcg/cm^2of parthenolide, which corresponds to 2 mcg of parthenolide per patch. Allergies to parthenolide occur frequently in gardeners and greenhouse employees, but non-occupational contact with plants and herbal teas containing sesquiterpenes also occurs.

Disperse Blue 106 (DB106) (Position 35):

Disperse blue 106 (purity ≥ 90%) is a commonly used thiazol-azoyl-p-phenylene diamine derivative dye used primarily in synthetic textiles and is a significant skin sensitization hazard. The product is formulated to contain 50 mcg/cm^2of disperse blue 106, which corresponds to 41 mcg of disperse blue 106 per patch. The gel vehicle is povidone. Together with Disperse blue 124, it has been determined to be the primary cause of textile dermatitis.

2-Bromo-2-nitropropane-1,3-diol (Bronopol) (Position 36):

2-Bromo-2-nitropropane-1,3-diol (purity ≥ 95%) is an antimicrobial agent commonly used as a preservative in many types of cosmetics, personal care products, and topical medications. The gel vehicle is povidone. The product is formulated to contain 250 mcg/cm^2of 2-Bromo-2-nitropropane-1,3-diol, which corresponds to 203 mcg of 2-Bromo-2-nitropropane-1,3-diol per patch.

12 CLINICAL PHARMACOLOGY

12.1 Mechanism of Action

A positive response to the patch test is a classic delayed cell-mediated hypersensitivity reaction (type IV), which normally appears within 9 to 96 hours after exposure. Following primary contact, an allergen penetrates the skin and binds covalently or noncovalently to epidermal Langerhans cells. The processed allergen is presented to helper T-lymphocytes, resulting in inflammation that produces a papular, vesicular, or bullous response with erythema and itching at the site of application.

14 CLINICAL STUDIES

A basic description of the interpretation method used by study personnel to evaluate the patch reactions obtained during the clinical studies is as follows [see Dosage and Administration (2)]:

 | ? | Doubtful reaction
 | + | Weak positive reaction
 | ++ | Strong positive reaction
 | +++ | Extreme positive reaction
 | - | Negative reaction
 | IR | Irritant reaction

14.1 Adults

Ten (10) studies were conducted in North America and Europe to evaluate the effectiveness, frequency of patch reactions, and/or sensitivity and specificity, and/or agreement with a reference allergen (when used) of T.R.U.E. TEST used to diagnosis allergic reactions to one or more allergens and or allergen mixes in the panels in adults. Subjects ranged in age from 18 through 86 years. Subjects with suspected allergic contact dermatitis, based on history or clinical signs, were tested in all studies. The allergens tested in each of the studies are noted in Table 1 [see Adverse Reactions (6.1)].

Study No. 1

This study evaluated the efficacy of T.R.U.E. TEST Panel 1.1. A total of 127 subjects with suspected contact dermatitis were recruited. T.R.U.E. TEST Panel 1.1, containing 12 allergens (no negative control was on the original Panel 1) was applied to the subject's back and remained there for 48 hours. The results were evaluated after 48 and 72 to 96 hours. Forty-five (45) subjects showed a total of 65 reactions to 11 of the 12 allergens in Panel 1.1. There were positive test reactions to all allergens except potassium dichromate. See Table 4.

Study No. 2

This study evaluated the efficacy of T.R.U.E. TEST Panel 2.1. A total of 121 subjects with suspected contact dermatitis were recruited. T.R.U.E. TEST Panel 2.1, containing 11 allergens and a negative control, was applied to the subject's back and remained there for 48 hours. The results were evaluated after 72 to 96 hours. Thirty-two (32) subjects showed a total of 46 positive test reactions. There were positive responses to all of the allergens except quinoline mix and paraben mix. See Table 4.

Study No. 3

This study evaluated the efficacy of T.R.U.E. TEST Panels 1.1 and 2.1 in a North American patient population referred for patch testing. One hundred nineteen (119) subjects were enrolled. T.R.U.E. TEST Panels 1.1 and 2.1, containing 23 allergens and a negative control, were applied to the subject's back and remained there for 48 hours. The results were evaluated at 72 to 96 hours after application. Results show that 66 subjects had a total of 123 positive test reactions. There were positive test responses to all of the allergens. See Table 4.

Study No. 4

This study was an open, multicenter, study that evaluated the efficacy of T.R.U.E. TEST and obtained information on late reactions and persistent local responses at a Day 21 safety visit (see Table 2). A total number of 50 prospectively identified subjects with suspected contact dermatitis were recruited. The most common dermatitis site was the hand, and the most common dermatitis type was allergic. T.R.U.E. TEST Panels 1.1 and 2.1 (24 allergens or allergen mixes, no negative control) were applied to the subject's back and remained there for 48 hours. The results were evaluated after 72 to 96, 120, or 168 hours. Thirty-two (32) subjects showed a total of 66 reactions to 21 of the 24 allergens included in T.R.U.E. TEST. The following allergens gave no reactions: caine mix, epoxy resin, quinoline mix, and black rubber mix. See Table 4.

Study No. 5

This single-site study evaluated the sensitivity and specificity of T.R.U.E. TEST Panel 3 allergens diazolidinyl urea (DU) (Germall® II) and imidazolidinyl urea (IMID) (Germall® 115) for diagnosing allergic contact dermatitis in a North American patient population. Comparison of allergen reactivity between allergens in T.R.U.E. TEST and allergens in petrolatum were made. One hundred thirty (130) subjects were enrolled and included 100 consecutive subjects (subjects with a clinical history consistent with allergic contact dermatitis without a previous positive patch test reaction) and sensitive subjects with a previous positive patch test reaction to petrolatum-based DU (15 subjects) and IMID (15 subjects) allergens in the past 5 years and a clinical history of allergic contact dermatitis. T.R.U.E. TEST Panel 3 allergens DU and IMID were applied to the subject's back and remained there for 48 hours. Patch test reactions were evaluated at 72 to 96 hours and again 7 days after application using the study endpoints, including measurements of positive reaction frequency, specificity, sensitivity, and agreement estimate as shown in Table 4 for each allergen.

Study No. 6

This study evaluated the sensitivity and specificity of T.R.U.E. TEST Panel 3 allergens tixocortol-21-pivalate (TIX) and budesonide (BUD) for diagnosing allergic contact dermatitis in a North American patient population. Comparison of allergen reactivity between allergens in T.R.U.E. TEST and allergens in petrolatum were made. One hundred twenty-eight (128) subjects were enrolled and included 100 consecutive subjects (subjects with a clinical history consistent with allergic contact dermatitis without a previous positive patch test reaction) and sensitive subjects with a previous positive patch test reaction to petrolatum based TIX (9 subjects) and BUD (19 subjects) allergens in the past 5 years and clinical history of allergic contact dermatitis. T.R.U.E. TEST Panel 3 allergens TIX and BUD were applied to the subject's back and remained there for 48 hours. Patch test reactions were evaluated 72 to 96 hours and again 7 days after application for 94 subjects. Six (6) subjects were withdrawn at Visit 2 due to poor tape adhesion prior to Visit 2. Patch test reactions were evaluated using the study endpoints, including measurements of positive reaction frequency, specificity, sensitivity, and agreement estimate as shown in Table 4.

Study No. 7

This study evaluated the sensitivity and specificity of T.R.U.E. TEST Panel 3.1 allergens tixocortol-21-pivalate (TIX), Hydrocortisone-17-butyrate (H-17-B), and budesonide (BUD) for diagnosing allergic contact dermatitis in a European patient population. Comparison of allergen reactivity between allergens in T.R.U.E. TEST and allergens in petrolatum were made. The enrolled study population included 200 consecutive subjects (subjects with a clinical history consistent with allergic contact dermatitis without a previous positive patch test reaction). T.R.U.E. TEST allergens TIX, H-17-B, BUD, and the corresponding petrolatum reference allergens were applied to the subject's back and remained there for 48 hours. Patch test reactions were evaluated at 72 to 96 hours and again 7 days after application. Of the 200 consecutive subjects evaluated, 1 subject was withdrawn due to poor tape adhesion prior to Visit 2 and 1 subject was excluded due to no follow-up visits. Therefore, 198 subjects were included in the evaluation of TIX and BUD. In addition, 3 subjects were withdrawn due to the H-17-B reference allergen patch not being applied at the initial visit. Therefore, 195 subjects were included in the evaluation for H-17-B. Patch test reactions were evaluated using the study endpoints, including measurements of positive reaction frequency, specificity, sensitivity, and agreement estimate as shown in Table 4.

Study No. 8

This was an open label, prospective, multi-center (5 site) study that evaluated the sensitivity and specificity of gold sodium thiosulphate (GST), Hydrocortisone-17-butyrate (H-17-B), bacitracin, parthenolide, methyldibromo glutaronitrile (MDBGN), disperse blue 106 (DB106), and 2-bromo-2-nitropropane-1,3-diol (bronopol) in adult subjects with suspected contact dermatitis and in adult subjects with a known or suspected sensitization to at least 1 of the 7 allergens. Of the 235 enrolled subjects, 110 were consecutive subjects (subjects with a clinical history consistent with allergic contact dermatitis without a previous positive patch test reaction) and 125 were sensitive subjects (subjects with a previous positive patch test reaction to at least 1 of the 7 allergens). The frequencies of all patch test reactions for each allergen were tabulated at 72 to 96 hours.

The agreement between the T.R.U.E. TEST allergens and their corresponding reference allergens was generally high among subjects who were sensitive to each allergen as seen in Table 4. With the exception of MDBGN, subjects who had sensitivities to each individual allergen had similar reactions to both the T.R.U.E. TEST allergens and the corresponding reference allergens with percent agreements ranging from 75.0% (for bacitracin) to 94.4% (for parthenolide). The results for MDBGN in this study may be unreliable due to the presence of phenoxyethanol (PE) in the reference allergen. Specifically, PE is a recognized irritant. Results of frequency, specificity, sensitivity, and agreement estimate are shown in Table 4.

Study No. 9

This in-use study evaluated the relationship between reactions caused by a natural sensitizer, such as nickel containing costume jewelry, and T.R.U.E. TEST. Forty nine (49) subjects with a history of cutaneous reactions to jewelry were tested with T.R.U.E. TEST Panel 1.1. A medallion containing approximately 20% nickel served as a positive control. Reactions were evaluated 72 to 96 hours after application. In comparing the in-use test results, 35% of the T.R.U.E. TEST nickel patch positive results would have been considered false positives and 5.3% would have been considered false negatives. However, the results from this study may be unreliable. The metal composition of jewelry can vary greatly from manufacturer to manufacturer and thereby alter the bioavailability of the nickel ions. A different medallion could have produced either a greater or lesser correlation with T.R.U.E. TEST nickel patch. The comparatively large number of additional nickel positive results obtained with T.R.U.E. TEST may be true positives unresponsive to the particular medallion used in this study, although false positive reactions cannot be ruled out.

Study No. 10

The study was a Phase 4 postmarketing open label, non-randomized, non-blinded prospective study including nine subjects. All subjects had previous positive patch test results for Quaternium-15 (Q-15). The subjects were exposed to the T.R.U.E. TEST Q-15 patch at a concentration of 100 mcg/cm^2and daily applications of a topical product containing Q-15 after the completion of the patch test. Reactions were evaluated 72 to 96 hours after application. T.R.U.E. TEST detected Q-15 sensitivity in 87.50% (7/8) of the Q-15 allergic subjects while the topically applied lotion elicited a positive response in 50% (4/8) of the study population. One subject tested negative to both methods of Q-15 and was removed from the endpoint analysis.

Study Data

Table 4 presents the frequency of positive reactions to T.R.U.E. TEST in consecutive subjects (subjects with a clinical history consistent with allergic contact dermatitis without a previous positive patch test reaction) for each allergen. The frequency of positive reactions to T.R.U.E. TEST in consecutive subjects and sensitive subjects (subjects with a previous positive patch test reaction to a specific allergen or allergens) for Quaternium-15 are presented in Table 4. The sensitivity, specificity, and agreement estimate between each T.R.U.E. TEST allergen and the corresponding reference allergen (when used) are presented for consecutive subjects and sensitive subjects (when done) in Table 4.

Sensitivity was determined using the formula [TP / (TP + FN)] × 100, where TP (true positive) represented positive results for both the T.R.U.E. TEST allergen and the corresponding reference allergen, and FN (false negative) represented negative results for the T.R.U.E. TEST allergen and positive results for the corresponding reference allergen. Specificity was determined using the formula [TN / (TN + FP)] × 100, where TN (true negative) represented negative results for both the T.R.U.E. TEST allergen and the corresponding reference allergen, and FP (false positive) represented positive results for the T.R.U.E. TEST allergen and negative results for the corresponding reference allergen. The agreement estimate (with 95% confidence intervals), as well as overall percent agreement and Cohen's kappa statistic between the test site skin reactions obtained for each of the seven T.R.U.E. TEST Panel 3.2 allergens and the test site skin reactions obtained for their associated reference allergens in petrolatum or ethanol were calculated for all subjects combined, as well as for the populations of sensitive and consecutive subjects.

Table 6- Available Frequency, Sensitivity, Specificity, and Agreement Estimate of T.R.U.E. TEST Allergens
Panel 1.3
Nickel sulfate [No reference control allergen was used.] Position 1 (Studies 1, 3, 4 and 9)
Frequency from consecutive subjects only (%) | 90/345 (26.1)
Wool alcohols (Lanolin) Position 2 (Studies 2, 3, and 4)
Frequency from consecutive subjects only (%) | 4/290 (1.4)
Neomycin sulfate Position 3 (Studies 1, 3, 4, and 9)
Frequency from consecutive subjects only (%) | 16/345 (4.6)
Potassium dichromate Position 4 (Studies 1, 3, 4 and 9)
Frequency from consecutive subjects only (%) | 5/345 (1.4)
Caine mix Position 5 (Studies 1, 3, 4, and 9)
Frequency from consecutive subjects only (%) | 7/345 (2.0)
Fragrance mix Position 6 (Studies 1, 3, 4, and 9)
Frequency from consecutive subjects only (%) | 23/345 (6.7)
Colophony Position 7 (Studies 1, 3, 4, and 9)
Frequency from consecutive subjects only (%) | 11/345 (3.2)
Paraben mix Position 8 (Studies 1, 3, 4, and 9)
Frequency from consecutive subjects only (%) | 5/290 (1.7)
Balsam of peru Position 10 (Studies 1, 3, 4, and 9)
Frequency from consecutive subjects only (%) | 17/345 (4.9)
Ethylenediamine dihydrochloride Position 11 (Studies 1, 3, 4 and 9)
Frequency from consecutive subjects only (%) | 7/345 (2.0)
Cobalt dichloride Position 12 (Studies 1, 3, 4, and 9)
Frequency from consecutive subjects only (%) | 29/345 (8.4)
Panel 2.3
p-tert-Butylphenol formaldehyde resin Position 13 (Studies 2, 3, and 4)
Frequency from consecutive subjects only (%) | 9/290 (3.0)
Epoxy resin Position 14 (Studies 1, 3, 4, and 9)
Frequency from consecutive subjects only (%) | 5/345 (1.4)
Carba mix Position 15 (Studies 2, 3, and 4)
Frequency from consecutive subjects only (%) | 6/290 (2.1)
Black rubber mix Position 16 (Studies 2, 3, and 4)
Frequency from consecutive subjects only (%) | 4/290 (1.4)
Cl+ Me- isothiazolinone (MCI/MI) Position 17 (Studies 2, 3, and 4)
Frequency from consecutive subjects only (%) | 8/290 (2.8)
Quaternium-15 (Q-15) Position 18
Test on sensitive subjects (Study 10)
Frequency from consecutive subjects only (%) | 7/9 (77.8)
Test on consecutive subjects (Studies 2, 3, and 4)
Frequency from consecutive subjects only (%) | 21/290 (7.2)
Methyldibromo glutaronitrile (MDBGN) Position 19 (Study 8)
Test on sensitive subjects |  | Petrolatum-based MDBGN/PE [The reference allergen MDBGN was used at one site and MDBGN/PE was used at four sites.]
Test on sensitive subjects |  | Pos | Neg | Total
T.R.U.E. TEST Panel Allergen | Pos | 4 | 1 | 5
T.R.U.E. TEST Panel Allergen | Neg | 10 | 14 | 24
T.R.U.E. TEST Panel Allergen | Total | 14 | 15 | 29
Sensitivity (%) (95% CI) | 28.6 (8.4, 58.1)
Specificity (%) (95% CI) | 93.3 (68.1, 99.8)
Agreement (%) (95% CI) | 62.1 (42.3, 79.3)
Test on consecutive subjects |  | Petrolatum-based MDBGN/PE
Test on consecutive subjects |  | Pos | Neg | Total
T.R.U.E. TEST Panel Allergen | Pos | 1 | 0 | 1
T.R.U.E. TEST Panel Allergen | Neg | 5 | 104 | 109
T.R.U.E. TEST Panel Allergen | Total | 6 | 104 | 110
Frequency from consecutive subjects only (%) | 1/110 (0.9)
Sensitivity (%)(95% CI) | 16.7 (0.4, 64.1)
Specificity (%) (95% CI) | 100 (96.5, 100.0)
Agreement (%) (95% CI) | 95.5 (89.7, 98.5)
Phenylenediamine Position 20 (Studies 1, 3, 4, and 9)
Frequency from consecutive subjects only (%) | 13/345 (3.8)
Formaldehyde Position 21 (Studies 3 and 4)
Frequency from consecutive subjects only (%) | 10/169 (5.9)
Mercapto mix Position 22 (Studies 2, 3, and 4)
Frequency from consecutive subjects only (%) | 9/290 (3.1)
Thimerosal Position 23 (Studies 2, 3, and 4)
Frequency from consecutive subjects only (%) | 30/290 (10.3)
Thiuram mix Position 24 (Studies 1, 3, 4, and 9)
Frequency from consecutive subjects only (%) | 14/345 (4.1)
Panel 3.3
Diazolidinyl urea (DU) (Germall® II) Position 25 (Study 5)
Test on sensitive subjects |  | Petrolatum-based DU
Test on sensitive subjects |  | Pos | Neg | Total
T.R.U.E. TEST Allergen | Pos | 4 | 2 | 6
T.R.U.E. TEST Allergen | Neg | 2 | 7 | 9
T.R.U.E. TEST Allergen | Total | 6 | 9 | 15
Sensitivity (%)(95% CI) | 66.7 (22.3, 95.7)
Specificity (%) (95% CI) | 77.8 (40.0, 97.2)
Agreement (%) (95% CI) | 73.3 (44.9, 92.2)
Test on consecutive subjects |  | Petrolatum-based DU
Test on consecutive subjects |  | Pos | Neg | Total
T.R.U.E. TEST Allergen | Pos | 3 | 1 | 4
T.R.U.E. TEST Allergen | Neg | 3 | 91 | 94
T.R.U.E. TEST Allergen | Total | 6 | 92 | 98
Frequency from consecutive subjects only (%) | 4 /98 (4.1)
Sensitivity (%)(95% CI) | 50 (11.8, 88.2)
Specificity (%) (95% CI) | 98.9 (94.1, 100.0)
Agreement (%) (95% CI) | 95.9 (89.9, 98.9)
Quinoline mix Position 26 (Studies 2, 3, and 4)
Frequency from consecutive subjects only (%) | 2/290 (0.7)
Tixocortol-21-pivalate (TIX) Position 27 (Studies 6 and 7 [Only consecutive subjects were evaluated in Study 7.])
Test on sensitive subjects |  | Petrolatum-based TIX
Test on sensitive subjects |  | Pos | Neg | Total
T.R.U.E. TEST Allergen | Pos | 7 | 1 | 8
T.R.U.E. TEST Allergen | Neg | 0 | 1 | 1
T.R.U.E. TEST Allergen | Total | 7 | 2 | 9
Sensitivity (%)(95% CI) | 100 (59.0, 100.0)
Specificity (%) (95% CI) | 50 (1.3, 98.7)
Agreement (%) (95% CI) | 88.9 (51.8, 99.7)
Test on consecutive subjects |  | Petrolatum-based TIX
Test on consecutive subjects |  | Pos | Neg | Total
T.R.U.E. TEST Allergen | Pos | 5 | 4 | 9
T.R.U.E. TEST Allergen | Neg | 1 | 282 | 283
T.R.U.E. TEST Allergen | Total | 6 | 286 | 292
Frequency from consecutive subjects only (%) | 9/292 (3.1)
Sensitivity (%)(95% CI) | 83.3 (35.9, 99.6)
Specificity (%) (95% CI) | 98.6 (96.5, 99.6)
Agreement (%) (95% CI) | 98.3 (96.0, 99.4)
Gold sodium thiosulfate (GST) Position 28 (Study 8)
Test on sensitive subjects |  | Petrolatum-based GST
Test on sensitive subjects |  | Pos | Neg | Total
T.R.U.E. TEST Allergen | Pos | 12 | 3 | 15
T.R.U.E. TEST Allergen | Neg | 0 | 4 | 4
T.R.U.E. TEST Allergen | Total | 12 | 7 | 19
Sensitivity (%)(95% CI) | 100 (73.5, 100.0)
Specificity (%) (95% CI) | 57.1 (18.4, 90.1)
Agreement (%) (95% CI) | 84.2 (60.4, 96.6)
Test on consecutive subjects |  | Petrolatum-based GST
Test on consecutive subjects |  | Pos | Neg | Total
T.R.U.E. TEST Allergen | Pos | 11 | 17 | 28
T.R.U.E. TEST Allergen | Neg | 0 | 82 | 82
T.R.U.E. TEST Allergen | Total | 11 | 99 | 110
Frequency from consecutive subjects only (%) | 28/110 (25.5)
Sensitivity (%)(95% CI) | 100 (71.5, 100.0)
Specificity (%) (95% CI) | 82.8 (73.9, 89.7)
Agreement (%) (95% CI) | 84.5 (76.4, 90.7)
Imidazolidinyl urea (IMID) (Germall 115®) Position 29 (Study 5)
Test on sensitive subjects |  | Petrolatum-based IMID
Test on sensitive subjects |  | Pos | Neg | Total
T.R.U.E. TEST Allergen | Pos | 3 | 1 | 4
T.R.U.E. TEST Allergen | Neg | 2 | 9 | 11
T.R.U.E. TEST Allergen | Total | 5 | 10 | 15
Sensitivity (%)(95% CI) | 60 (14.7, 94.7)
Specificity (%) (95% CI) | 90 (55.5, 99.7)
Agreement (%) (95% CI) | 80.0 (51.9, 95.7)
Test on consecutive subjects |  | Petrolatum-based IMID
Test on consecutive subjects |  | Pos | Neg | Total
T.R.U.E. TEST Allergen | Pos | 3 | 0 | 3
T.R.U.E. TEST Allergen | Neg | 3 | 92 | 95
T.R.U.E. TEST Allergen | Total | 6 | 92 | 98
Frequency from consecutive subjects only (%) | 3/98 (3.1)
Sensitivity (%)(95% CI) | 50 (11.8, 88.2)
Specificity (%) (95% CI) | 100 (96.1, 100.0)
Agreement (%) (95% CI) | 96.9 (91.3, 99.4)
Budesonide (BUD) Position 30 (Study 6 and 7)
Test on sensitive subjects |  | Petrolatum-based budesonide
Test on sensitive subjects |  | Pos | Neg | Total
T.R.U.E. TEST Allergen | Pos | 11 | 1 | 12
T.R.U.E. TEST Allergen | Neg | 1 | 6 | 7
T.R.U.E. TEST Allergen | Total | 12 | 7 | 19
Sensitivity (%)(95% CI) | 91.7 (61.5, 99.8)
Specificity (%) (95% CI) | 85.7 (42.1, 99.6)
Agreement (%) (95% CI) | 89.5 (66.9, 98.7)
Test on consecutive subjects |  | Petrolatum-based budesonide
Test on consecutive subjects |  | Pos | Neg | Total
T.R.U.E. TEST Allergen | Pos | 2 | 1 | 3
T.R.U.E. TEST Allergen | Neg | 0 | 289 | 289
T.R.U.E. TEST Allergen | Total | 2 | 290 | 292
Frequency from consecutive subjects only (%) | 3/292 (1.0)
Sensitivity (%)(95% CI) | 100 (15.8, 100.0)
Specificity (%) (95% CI) | 99.7 (98.1, 100.0)
Agreement (%) (95% CI) | 99.7 (98.1, 100.0)
Hydrocortisone-17-butyrate (H-17-B) Position 31 (Studies 7 and 8)
Test on sensitive subjects |  | Ethanol-based H-17-B
Test on sensitive subjects |  | Pos | Neg | Total
T.R.U.E. TEST Allergen | Pos | 12 | 1 | 13
T.R.U.E. TEST Allergen | Neg | 1 | 6 | 7
T.R.U.E. TEST Allergen | Total | 13 | 7 | 20
Sensitivity (%)(95% CI) | 92.3 (64.0, 99.8)
Specificity (%) (95% CI) | 85.7 (42.1, 99.6)
Agreement (%) (95% CI) | 90.0 (68.3, 98.8)
Test on consecutive subjects |  | Ethanol-based H-17-B
Test on consecutive subjects |  | Pos | Neg | Total
T.R.U.E. TEST Allergen | Pos | 0 | 0 | 0
T.R.U.E. TEST Allergen | Neg | 1 | 304 | 305
T.R.U.E. TEST Allergen | Total | 1 | 304 | 305
Frequency from consecutive subjects only (%) | 0/305 (0.0)
Sensitivity (%)(95% CI) | 0 (0.0, 97.5)
Specificity (%) (95% CI) | 100 (98.8, 100.0)
Agreement (%) (95% CI) | 99.7 (98.2, 100.0)
Mercaptobenzothiazole Position 32 (Studies 2, 3, and 4)
Frequency from consecutive subjects only (%) | 8/290 (2.8)
Bacitracin Position 33 (Study 8)
Test on sensitive subjects |  | Petrolatum-based bacitracin
Test on sensitive subjects |  | Pos | Neg | Total
T.R.U.E. TEST Allergen | Pos | 13 | 5 | 18
T.R.U.E. TEST Allergen | Neg | 1 | 5 | 6
T.R.U.E. TEST Allergen | Total | 14 | 10 | 24
Sensitivity (%)(95% CI) | 92.9 (66.1, 99.8)
Specificity (%) (95% CI) | 50 (18.7, 81.3)
Agreement (%) (95% CI) | 75.0 (53.3, 90.2)
Test on consecutive subjects |  | Petrolatum-based bacitracin
Test on consecutive subjects |  | Pos | Neg | Total
T.R.U.E. TEST Panel Allergen | Pos | 5 | 0 | 5
T.R.U.E. TEST Panel Allergen | Neg | 1 | 104 | 105
T.R.U.E. TEST Panel Allergen | Total | 6 | 104 | 110
Frequency from consecutive subjects only (%) | 5/110 (4.5)
Sensitivity (%)(95% CI) | 83.3 (35.9, 99.6)
Specificity (%) (95% CI) | 100 (96.5, 100.0)
Agreement (%) (95% CI) | 99.1 (95.0, 100.0)
Parthenolide Position 34 (Study 8)
Test on sensitive subjects |  | Petrolatum-based parthenolide
Test on sensitive subjects |  | Pos | Neg | Total
T.R.U.E. TEST Allergen | Pos | 13 | 0 | 13
T.R.U.E. TEST Allergen | Neg | 1 | 4 | 5
T.R.U.E. TEST Allergen | Total | 14 | 4 | 18
Sensitivity (%)(95% CI) | 92.9 (66.1, 99.8)
Specificity (%) (95% CI) | 100 (39.8, 100.0)
Agreement (%) (95% CI) | 94.4 (72.7, 99.9)
Test on consecutive subjects |  | Petrolatum-based parthenolide
Test on consecutive subjects |  | Pos | Neg | Total
T.R.U.E. TEST Panel Allergen | Pos | 1 | 0 | 1
T.R.U.E. TEST Panel Allergen | Neg | 0 | 109 | 109
T.R.U.E. TEST Panel Allergen | Total | 1 | 109 | 110
Frequency from consecutive subjects only (%) | 1/110 (0.9)
Sensitivity (%)(95% CI) | 100 (2.5, 100.0)
Specificity (%) (95% CI) | 100 (96.7, 100.0)
Agreement (%) (95% CI) | 100.0 (96.7, 100.0)
Disperse blue 106 (DB106) Position 35 (Study 8)
Test on sensitive subjects |  | Petrolatum-based DB106
Test on sensitive subjects |  | Pos | Neg | Total
T.R.U.E. TEST Allergen | Pos | 8 | 1 | 9
T.R.U.E. TEST Allergen | Neg | 1 | 7 | 8
T.R.U.E. TEST Allergen | Total | 9 | 8 | 17
Sensitivity (%)(95% CI) | 88.9 (51.8, 99.7)
Specificity (%) (95% CI) | 87.5 (47.3, 99.7)
Agreement (%) (95% CI) | 88.2 (63.6, 98.5)
Test on consecutive subjects |  | Petrolatum-based DB106
Test on consecutive subjects |  | Pos | Neg | Total
T.R.U.E. TEST Panel Allergen | Pos | 1 | 0 | 1
T.R.U.E. TEST Panel Allergen | Neg | 0 | 109 | 109
T.R.U.E. TEST Panel Allergen | Total | 1 | 109 | 110
Frequency from consecutive subjects only (%) | 1/110 (0.9)
Sensitivity (%)(95% CI) | 100 (2.5, 100.0)
Specificity (%) (95% CI) | 100 (96.7, 100.0)
Agreement (%) (95% CI) | 100.0 (96.7, 100.0)
2-Bromo-2-nitropropane-1,3-diol (Bronopol) Position 36 (Study 8)
Test on sensitive subjects |  | Petrolatum-based Bronopol
Test on sensitive subjects |  | Pos | Neg | Total
T.R.U.E. TEST Allergen | Pos | 4 | 4 | 8
T.R.U.E. TEST Allergen | Neg | 0 | 15 | 15
T.R.U.E. TEST Allergen | Total | 4 | 19 | 23
Sensitivity (%)(95% CI) | 100 (39.8, 100.0)
Specificity (%) (95% CI) | 78.9 (54.4, 93.9)
Agreement (%) (95% CI) | 82.6 (61.2, 95.0)
Test on consecutive subjects |  | Petrolatum-based Bronopol
Test on consecutive subjects |  | Pos | Neg | Total
T.R.U.E. TEST Panel Allergen | Pos | 1 | 2 | 3
T.R.U.E. TEST Panel Allergen | Neg | 0 | 107 | 107
T.R.U.E. TEST Panel Allergen | Total | 1 | 109 | 110
Frequency from consecutive subjects only (%) | 3/110 (2.7)
Sensitivity (%)(95% CI) | 100 (2.5, 100.0)
Specificity (%) (95% CI) | 98.2 (93.5, 99.8)
Agreement (95% CI) | 98.2 (93.6, 99.8)
** Dose and/or excipients may have changed from clinical study product reported to finished product.

14.2 Children and Adolescents 6 through 17 Years of Age

Two studies were conducted in the US to evaluate the diagnostic performance of T.R.U.E. TEST in children and adolescents 6 through 17 years of age. Subjects had three T.R.U.E. TEST panels applied to their back or upper arm for 48 hours. Reactions at the patch test sites were evaluated at days 3 and/or 4, 7 and 21 after patch test application [see Interpretation Instructions (2.4)].

Pediatric Study 1

In an open-label, prospective, single-center study conducted in the US, 102 children and adolescents 6 through 17 years of age with suspected allergic contact dermatitis were enrolled to evaluate the diagnostic performance of a previously approved version of T.R.U.E. TEST (Panels 1.1, 2.1, 3.1). This version included a negative control and 28 allergens and allergen mixes, 4 (on Panel 1.1) of which were reformulated and are not included on Panel 1.3 .The per-protocol analysis set included 100 subjects. The frequencies of positive reactions to the 24 allergens contained in T.R.U.E. TEST and to the negative controls are shown in Table 7.

Pediatric Study 2

In an open-label, prospective, multi-center study conducted in the US, 116 children and adolescents 6 through 17 years of age with suspected allergic contact dermatitis were enrolled. Although the three T.R.U.E. TEST panels administered to subjects in this study included all 35 allergens and allergen mixes, the primary analysis of diagnostic performance was limited to the 4 reformulations and the 7 new allergens and allergen mixes. The frequencies of positive reactions to 11 of the allergens contained in T.R.U.E. TEST and to the negative control were analyzed and are shown in Table 7.

Table 7- Pediatric Studies 1 [NCT: 00795951] and 2 [NCT: 01797562] : Frequencies of Positive Reactions [In Pediatric Studies 1 and 2, positive patch reactions were read on days 3, 4, and 7. Frequencies of positive reactions reported in this table include those characterized as weak (+), strong (++), and extreme positive (+++) based on presence and degree of erythema, infiltration, papules, vesicles, and bullae.] (on Days 3, 4, and 7 After T.R.U.E. TEST Application) to T.R.U.E. TEST Allergens Among Children and Adolescents 6 through 17 Years of Age with Suspected Allergic Contact Dermatitis: Per Protocol Analysis Sets
 |  | Pediatric Study 1 | Pediatric Study 2
 |  | N=100 | N=53 [Only 53 subjects in Pediatric Study 2 in the per-protocol analysis set received Panel 1.3.]
Panel | Allergen | n (%) | n (%)
Panel 1.3 | 1. Nickel Sulfate | 30 (30.0) | NA [NA= Not Applicable/Not Available.The results are not applicable because the allergens and allergen mixes were either from previously approved formulations, not evaluated or not pre-specified as the primary endpoint of the study.]
Panel 1.3 | 2. Wool Alcohols | 16 (16.0) | NA
Panel 1.3 | 3. Neomycin Sulfate | NA | 2 (3.8)
Panel 1.3 | 4. Potassium Dichromate | NA | 2 (3.8)
Panel 1.3 | 5. Caine Mix | 0 (0.0) | NA
Panel 1.3 | 6. Fragrance Mix | NA | 2 (3.8)
Panel 1.3 | 7. Colophony | 9 (9.0) | NA
Panel 1.3 | 8. Paraben Mix | 2 (2.0) | NA
Panel 1.3 | 9. Negative Control | 0 (0.0) | NA
Panel 1.3 | 10. Balsam of Peru | 10 (10.0) | NA
Panel 1.3 | 11. Ethylenediamine Dihydrochloride | NA | 0 (0.0)
Panel 1.3 | 12. Cobalt Dichloride | 13 (13.0) | NA
 |  | N=100 | N=111
Panel 2.3 | 13. p-tert-Butylphenol Formaldehyde Resin | 17 (17.0) | NA
Panel 2.3 | 14. Epoxy Resin | 4 (4.0) | NA
Panel 2.3 | 15. Carba Mix | 7 (7.0) | NA
Panel 2.3 | 16. Black Rubber Mix | 2 (2.0) | NA
Panel 2.3 | 17. Cl+Me-Isothiazolinone (MCI/MI) | 4 (4.0) | NA
Panel 2.3 | 18. Quaternium-15 | 4 (4.0) | NA
Panel 2.3 | 19. Methyldibromo Glutaronitrile (MDBGN) | NA | 1 (0.9)
Panel 2.3 | 20. p-Phenylenediamine | 2 (2.0) | NA
Panel 2.3 | 21. Formaldehyde | 7 (7.0) | NA
Panel 2.3 | 22. Mercapto Mix | 2 (2.0) | NA
Panel 2.3 | 23. Thimerosal | 4 (4.0) | NA
Panel 2.3 | 24. Thiuram Mix | 7 (7.0) | NA
Panel 3.3 . | 25. Diazolidinyl urea | 5 (5.0) | NA
Panel 3.3 . | 26. Imidazolidinyl urea | 2 (2.0) | NA
Panel 3.3 . | 27. Budesonide | 1 (1.0) | NA
Panel 3.3 . | 29. Quinoline Mix | 1 (1.0) | NA
Panel 3.3 . | 28. Tixocortol-21-pivalate | 8 (8.0) | NA
Panel 3.3 . | 28. Gold Sodium Thiosulfate (GST) | NA | 30 (27.0)
Panel 3.3 . | 31. Hydrocortisone-17-Butyrate (H-17-B) | NA | 2 (1.8)
Panel 3.3 . | 19. & 32. Mercaptobenzothiazole | 2 (2.0) | NA
Panel 3.3 . | 33. Bacitracin | NA | 14 (12.6)
Panel 3.3 . | 34. Parthenolide | NA | 8 (7.2)
Panel 3.3 . | 35. Disperse Blue 106 | NA | 4 (3.6)
Panel 3.3 . | 36. 2-Bromo-2-nitropane-1,3-diol (Bronopol) | NA | 19 (17.1)

16 HOW SUPPLIED/STORAGE AND HANDLING

A multipack carton contains five units. Each unit consists of three adhesive panels, each containing 12 patches - NDC 67334-0457-1.

STORAGE AND HANDLING

Store T.R.U.E. TEST between 2° and 8°C (36° and 46°F). Refrigeration required. Do not freeze. Failure to store T.R.U.E. TEST as recommended may result in loss of potency and inaccurate test results.

17 PATIENT COUNSELING INFORMATION

Inform the patient of the following:

- Patients should seek immediate medical attention and contact their healthcare provider if they experience symptoms of a severe allergic reaction such as trouble breathing or wheezing; a swollen tongue or throat; a drop in blood pressure resulting in dizziness or fainting; a weak and rapid pulse; hives or widespread itching [see Warnings and Precautions (5.1)].
- Patients may remove the panels themselves if advised by their healthcare provider to do so or if they are experiencing systemic symptom [see Warnings and Precautions (5.1)].
- Itching and burning sensations are common with patch testing and may be severe in extremely sensitive patients.
- Avoid UV exposure and tanning beds [see Dosage and Administration (2.1)].
- Patients should report to their physician any reactions at the patch test site occurring seven or more days after panel removal to identify potential late or persistent reactions or possible sensitizations [see Warnings and Precautions (5.2, 5.7, 5.8) and Dosage and Administration (2.2)] .
- p-Phenylenediamine and disperse blue 106 (DB106) are dyes and may leave a dark spot on the skin at the allergen location. This is not an allergic reaction. This discoloration may remain for approximately two weeks.
- Avoid getting the panels and surrounding area wet [see Dosage and Administration (2.1)].
- Patients should avoid physical activity that may result in reduced adhesion or actual loss of the test panels [see Dosage and Administration (2.1)].
- Patients should avoid excessive sweating and keep the test panels and surrounding area dry [see Dosage and Administration (2.1)].

Manufactured by SmartPractice Denmark ApS
Hillerød, Denmark
U.S. License No. 1888
Distributed by SmartPractice
Phoenix, AZ 85008
US Patents 4,836,217 and 5,182,081, 5,614,167

THIN-LAYER RAPID USE
EPICUTANEOUS PATCH TEST
T.R.U.E. TEST ®
NDC: 67334-0457-1

For further details of allergen constituents and dose, see outer box.

Rx only
For Topical Use Only

Store between 2° and 8°C (36° and 46°F).

PANEL 1.3

Application Instructions

Peel open the package and remove the test panel.

Remove the protective plastic covering from the test surface of the panel. Be careful not to touch the test substances.

Position test Panel 1.3 on the patient's back. Allergen number 1 should be in the upper left corner. Avoid applying the panel on the margin of the scapula or directly over the midline of the spine. Ensure that each patch of the allergen panel is in contact with the skin by smoothing the panel outward from the center to the edge.

With a medical marking pen, indicate on the skin the location of the two notches on the panel.

Store between 2° and 8°C (36° and 46°F).
Refrigeration required. Do not freeze.

Manufactured by SmartPractice Denmark ApS
Hillerød, Denmark
US License No. 1888

Distributed by SmartPractice®
Phoenix, AZ 85008
Made in Denmark

51-2009-00/1

THIN-LAYER RAPID USE
EPICUTANEOUS PATCH TEST
T.R.U.E. TEST ®
NDC: 67334-0457-1

For further details of allergen constituents and dose, see outer box.

Rx only

For Topical Use Only

Store between 2° and 8°C (36° and 46°F).

PANEL 2.3

Application Instructions

A desiccant is included in this package for stability purposes.

Peel open the package and remove the test panel.

Remove the protective plastic covering from the test surface of the panel. Be careful not to touch the test substances.

Position test Panel 2.3 on the patient's back. Allergen number 13 should be in the upper left corner. Avoid applying the panel on the margin of the scapula or directly over the midline of the spine. Ensure that each patch of the allergen panel is in contact with the skin by smoothing the panel outward from the center to the edge.

With a medical marking pen, indicate on the skin the location of the two notches on the panel.

Store between 2° and 8°C (36° and 46°F).
Refrigeration required. Do not freeze.

Manufactured by SmartPractice Denmark ApS
Hillerød, Denmark
US License No. 1888

Distributed by SmartPractice®
Phoenix, AZ 85008
Made in Denmark

51-2012-00/2

THIN-LAYER RAPID USE
EPICUTANEOUS PATCH TEST
T.R.U.E. TEST ®
NDC: 67334-0457-1

For further details of allergen constituents and dose, see outer box.

Rx only
For Topical Use Only

Store between 2° and 8°C (36° and 46°F).

PANEL 3.3

Application Instructions

Peel open the package and remove the test panel.

Remove the protective plastic covering from the test surface of the panel. Be careful not to touch the test substances.

Position test panel 3.3 on the patient's back. Allergen number 25 should be in the upper left corner. Avoid applying the panel on the margin of the scapula or directly over the midline of the spine. Ensure that each patch of the allergen panel is in contact with the skin by smoothing the panel outward from the center to the edge.

With a medical marking pen, indicate on the skin the location of the two notches on the panel.

Store between 2° and 8°C (36° and 46°F).
Refrigeration required. Do not freeze.

Manufactured by SmartPractice Denmark ApS
Hillerød, Denmark
US License No. 1888

Distributed by SmartPractice®
Phoenix, AZ 85008
Made in Denmark

51-2015-00/1

INSTRUCTIONS FOR USE

Panel 1.3

THIN-LAYER RAPID USE
EPICUTANEOUS PATCH TEST
T.R.U.E. TEST ®

Manufactured by SmartPractice Denmark ApS
Distributed by SmartPractice®
Made in Denmark

52-5115-00/1

INSTRUCTIONS FOR USE

Panel 2.3

THIN-LAYER RAPID USE
EPICUTANEOUS PATCH TEST
T.R.U.E. TEST ®

Manufactured by SmartPractice Denmark ApS
Distributed by SmartPractice®
Made in Denmark

52-5115-00/1

INSTRUCTIONS FOR USE

Panel 3.3

THIN-LAYER RAPID USE
EPICUTANEOUS PATCH TEST
T.R.U.E. TEST ®

Manufactured by SmartPractice Denmark ApS
Distributed by SmartPractice®
Made in Denmark

52-5125-00/1

PRINCIPAL DISPLAY PANEL - Kit Carton

THIN-LAYER RAPID USE
EPICUTANEOUS PATCH TEST

T.R.U.E. TEST®

NDC No: 67334-0457-5 |  |  | Mcg/cm^2
PANEL 1.3 | 1 | Nickel Sulfate | 200
PANEL 1.3 | 2 | Wool Alcohols | 1000
 | 3 | Neomycin Sulfate | 600
 | 4 | Potassium Dichromate | 54
 | 5 | Caine Mixa | 630
 | 6 | Fragrance Mixb | 500
 | 7 | Colophony | 1200
 | 8 | Paraben Mixc | 1000
 | 9 | Negative Control | —
 | 10 | Balsam of Peru | 800
 | 11 | Ethylenediamine Dihydrochloride | 50
 | 12 | Cobalt Dichloride | 20
 | 13 | p-tert-Butylphenol Formaldehyde Resin | 45
PANEL 2.3 | 14 | Epoxy Resin | 50
PANEL 2.3 | 15 | Carba Mixd | 250
 | 16 | Black Rubber Mixe | 75
 | 17 | Cl^+Me^-Isothiazolinone | 4
 | 18 | Quaternium-15 | 100
 | 19 | Methyldibromo Glutaronitrile | 5
 | 20 | p-Phenylenediamine | 80
 | 21 | Formaldehydef | 180
 | 22 | Mercapto Mixg | 75
 | 23 | Thimerosal | 7
 | 24 | Thiuram Mixh | 27
 | 25 | Diazolidinyl Urea | 550
 | 26 | Quinoline Mixi | 190
 | 27 | Tixocortol-21-Pivalate | 3
PANEL 3.3 | 28 | Gold Sodium Thiosulfate | 75
PANEL 3.3 | 29 | Imidazolidinyl Urea | 600
 | 30 | Budesonide | 1
 | 31 | Hydrocortisone-17-Butyrate | 20
 | 32 | Mercaptobenzothiazole | 75
 | 33 | Bacitracin | 600
 | 34 | Parthenolide | 3
 | 35 | Disperse blue 106 | 50
 | 36 | 2-Bromo-2-Nitropropane-1,3-diol | 250

Each unit contains panel 1.3, panel 2.3 and panel 3.3.
A desiccant is included in panel 2.3 package for stability purposes.
Concentrations expressed in micrograms/centimeter squared.
Notations a-i are located on the back panel.

Rx only
For Topical Use Only

Store between 2° and 8°C
(36° and 46°F).
Refrigeration required.
Do not freeze.

5
Units

PUSH
TO OPEN